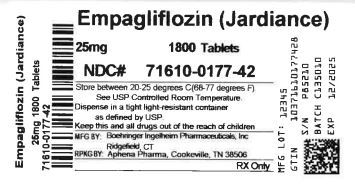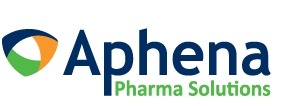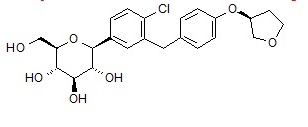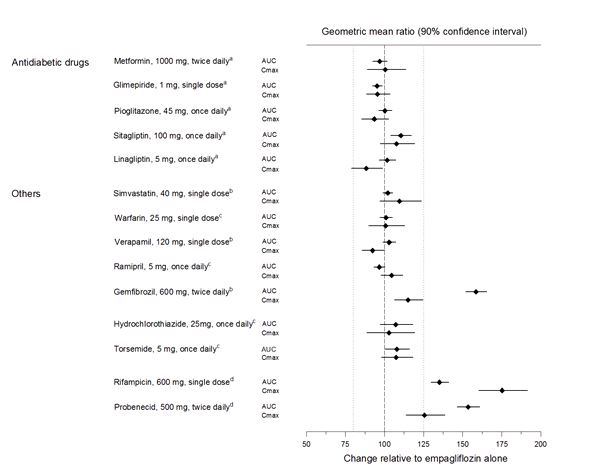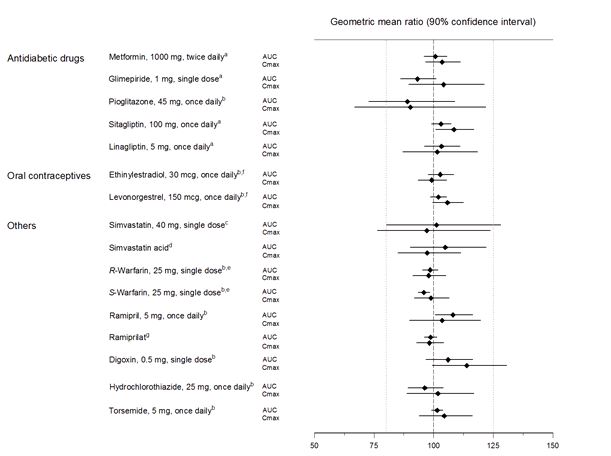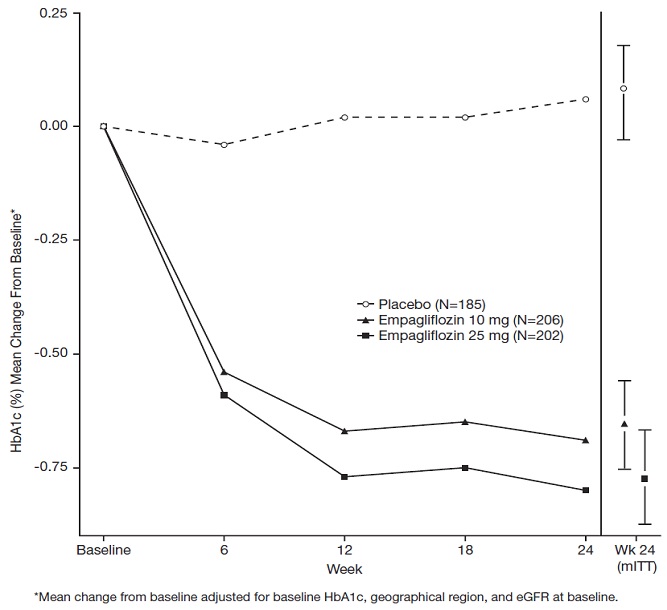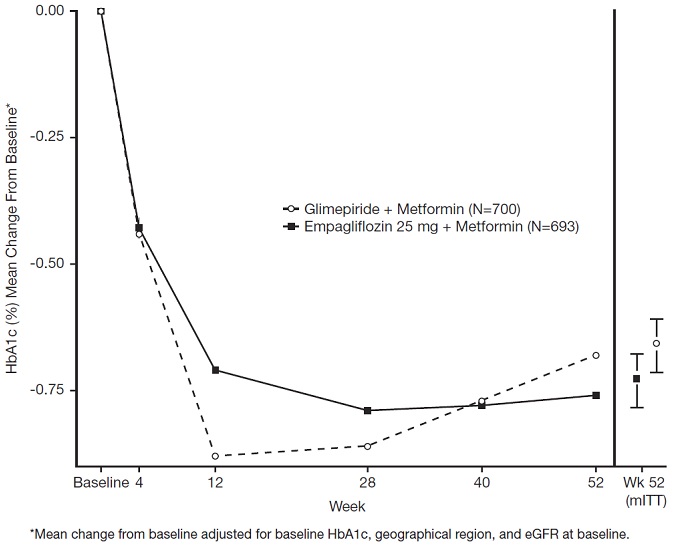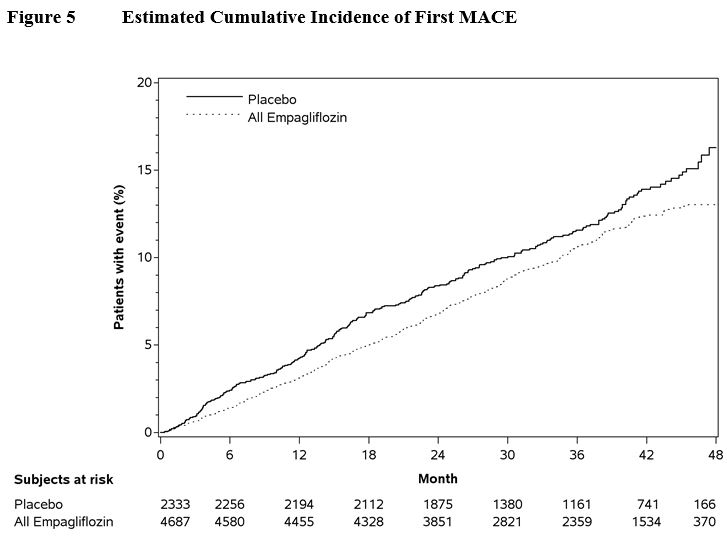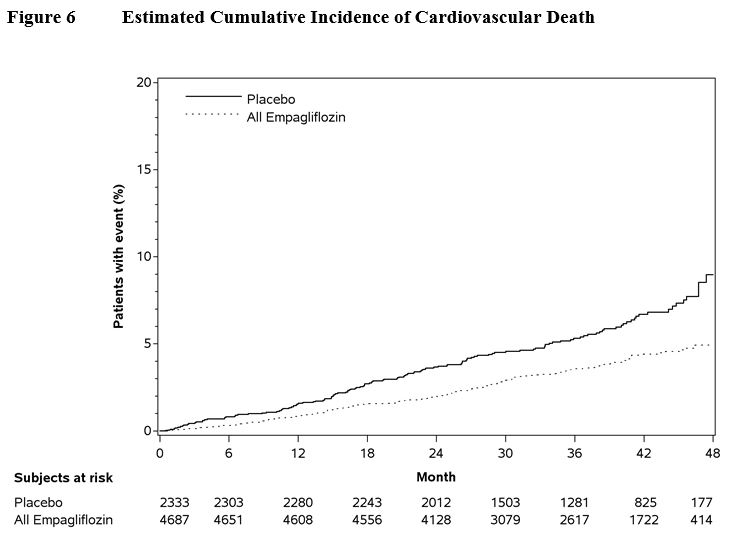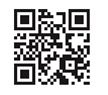 DRUG LABEL: Jardiance
NDC: 71610-177 | Form: TABLET, FILM COATED
Manufacturer: Aphena Pharma Solutions - Tennessee, LLC
Category: prescription | Type: HUMAN PRESCRIPTION DRUG LABEL
Date: 20251027

ACTIVE INGREDIENTS: EMPAGLIFLOZIN 25 mg/1 1

HIGHLIGHTS OF PRESCRIBING INFORMATION

These highlights do not include all the information needed to use JARDIANCE safely and effectively. See full prescribing information for JARDIANCE.
JARDIANCE®(empagliflozin) tablets, for oral use
Initial U.S. Approval: 2014

RECENT MAJOR CHANGES

Contraindications (4) | 12/2017
Warnings and Precautions (5) | 12/2017

1 INDICATIONS AND USAGE

JARDIANCE is a sodium-glucose co-transporter 2 (SGLT2) inhibitor indicated:

- as an adjunct to diet and exercise to improve glycemic control in adults with type 2 diabetes mellitus,
- to reduce the risk of cardiovascular death in adult patients with type 2 diabetes mellitus and established cardiovascular disease. (1)

Limitations of Use: Not for the treatment of type 1 diabetes mellitus or diabetic ketoacidosis (1)

2 DOSAGE AND ADMINISTRATION

- The recommended dose of JARDIANCE is 10 mg once daily, taken in the morning, with or without food (2.1)
- Dose may be increased to 25 mg once daily (2.1)
- Assess renal function before initiating JARDIANCE. Do not initiate JARDIANCE if eGFR is below 45 mL/min/1.73 m^2(2.2)
- Discontinue JARDIANCE if eGFR falls persistently below 45 mL/min/1.73 m^2(2.2)

3 DOSAGE FORMS AND STRENGTHS

Tablets: 10 mg, 25 mg (3)

4 CONTRAINDICATIONS

- History of serious hypersensitivity reaction to empagliflozin or any of the excipients in JARDIANCE (4)
- Severe renal impairment, end-stage renal disease, or dialysis (4)

5 WARNINGS AND PRECAUTIONS

- Hypotension:Before initiating JARDIANCE assess and correct volume status in patients with renal impairment, the elderly, in patients with low systolic blood pressure, and in patients on diuretics. Monitor for signs and symptoms during therapy. (5.1)
- Ketoacidosis:Assess patients who present with signs and symptoms of metabolic acidosis for ketoacidosis, regardless of blood glucose level. If suspected, discontinue JARDIANCE, evaluate and treat promptly. Before initiating JARDIANCE, consider risk factors for ketoacidosis. Patients on JARDIANCE may require monitoring and temporary discontinuation of therapy in clinical situations known to predispose to ketoacidosis. (5.2)
- Acute kidney injury and impairment in renal function:Consider temporarily discontinuing in settings of reduced oral intake or fluid losses. If acute kidney injury occurs, discontinue and promptly treat. Monitor renal function during therapy. (5.3)
- Urosepsis and Pyelonephritis:Evaluate patients for signs and symptoms of urinary tract infections and treat promptly, if indicated (5.4)
- Hypoglycemia:Consider lowering the dose of insulin secretagogue or insulin to reduce the risk of hypoglycemia when initiating JARDIANCE (5.5)
- Genital mycotic infections:Monitor and treat as appropriate (5.6)
- Hypersensitivity reactions:Discontinue JARDIANCE, treat promptly, and monitor until signs and symptoms resolve (5.7)
- Increased LDL-C:Monitor and treat as appropriate (5.8)

6 ADVERSE REACTIONS

- The most common adverse reactions associated with JARDIANCE (5% or greater incidence) were urinary tract infections and female genital mycotic infections (6.1)

To report SUSPECTED ADVERSE REACTIONS, contact Boehringer Ingelheim Pharmaceuticals, Inc. at 1-800-542-6257 or 1-800-459-9906 TTY, or FDA at 1-800-FDA-1088 or www.fda.gov/medwatch.

8 USE IN SPECIFIC POPULATIONS

- Pregnancy:Advise females of the potential risk to a fetus especially during the second and third trimesters (8.1)
- Lactation:JARDIANCE is not recommended when breastfeeding (8.2)
- Geriatric patients:Higher incidence of adverse reactions related to volume depletion and reduced renal function (5.1, 5.3, 8.5)
- Patients with renal impairment:Higher incidence of adverse reactions related to reduced renal function (2.2, 5.3, 8.6)

FULL PRESCRIBING INFORMATION

1 INDICATIONS AND USAGE

JARDIANCE is indicated:

- as an adjunct to diet and exercise to improve glycemic control in adults with type 2 diabetes mellitus,
- to reduce the risk of cardiovascular death in adult patients with type 2 diabetes mellitus and established cardiovascular disease.

Limitations of Use
JARDIANCE is not recommended for patients with type 1 diabetes or for the treatment of diabetic ketoacidosis.

2 DOSAGE AND ADMINISTRATION

2.1 Recommended Dosage

The recommended dose of JARDIANCE is 10 mg once daily in the morning, taken with or without food. In patients tolerating JARDIANCE, the dose may be increased to 25 mg [see Clinical Studies (14)] .

In patients with volume depletion, correcting this condition prior to initiation of JARDIANCE is recommended [see Warnings and Precautions (5.1), Use in Specific Populations (8.5) and Patient Counseling Information (17)].

2.2 Patients with Renal Impairment

Assessment of renal function is recommended prior to initiation of JARDIANCE and periodically thereafter.

JARDIANCE should not be initiated in patients with an eGFR less than 45 mL/min/1.73 m^2.

No dose adjustment is needed in patients with an eGFR greater than or equal to 45 mL/min/1.73 m^2.

JARDIANCE should be discontinued if eGFR is persistently less than 45 mL/min/1.73 m^2 [see Warnings and Precautions (5.1, 5.3) and Use in Specific Populations (8.6)] .

3 DOSAGE FORMS AND STRENGTHS

JARDIANCE tablets available as:

- 10 mg pale yellow, round, biconvex and bevel-edged, film-coated tablets debossed with “S 10” on one side and the Boehringer Ingelheim company symbol on the other side.
- 25 mg pale yellow, oval, biconvex, film-coated tablets debossed with “S 25” on one side and the Boehringer Ingelheim company symbol on the other side.

4 CONTRAINDICATIONS

- History of serious hypersensitivity reaction to empagliflozin or any of the excipients in JARDIANCE [see Warnings and Precautions (5.7)] .
- Severe renal impairment, end-stage renal disease, or dialysis [see Use in Specific Populations (8.6)] .

5 WARNINGS AND PRECAUTIONS

5.1 Hypotension

JARDIANCE causes intravascular volume contraction. Symptomatic hypotension may occur after initiating JARDIANCE [see Adverse Reactions (6.1)] particularly in patients with renal impairment, the elderly, in patients with low systolic blood pressure, and in patients on diuretics. Before initiating JARDIANCE, assess for volume contraction and correct volume status if indicated. Monitor for signs and symptoms of hypotension after initiating therapy and increase monitoring in clinical situations where volume contraction is expected [see Use in Specific Populations (8.5)] .

5.2 Ketoacidosis

Reports of ketoacidosis, a serious life-threatening condition requiring urgent hospitalization have been identified in postmarketing surveillance in patients with type 1 and type 2 diabetes mellitus receiving sodium glucose co-transporter-2 (SGLT2) inhibitors, including JARDIANCE. Fatal cases of ketoacidosis have been reported in patients taking JARDIANCE. JARDIANCE is not indicated for the treatment of patients with type 1 diabetes mellitus [see Indications and Usage (1)] .

Patients treated with JARDIANCE who present with signs and symptoms consistent with severe metabolic acidosis should be assessed for ketoacidosis regardless of presenting blood glucose levels, as ketoacidosis associated with JARDIANCE may be present even if blood glucose levels are less than 250 mg/dL. If ketoacidosis is suspected, JARDIANCE should be discontinued, patient should be evaluated, and prompt treatment should be instituted. Treatment of ketoacidosis may require insulin, fluid and carbohydrate replacement.

In many of the postmarketing reports, and particularly in patients with type 1 diabetes, the presence of ketoacidosis was not immediately recognized and institution of treatment was delayed because presenting blood glucose levels were below those typically expected for diabetic ketoacidosis (often less than 250 mg/dL). Signs and symptoms at presentation were consistent with dehydration and severe metabolic acidosis and included nausea, vomiting, abdominal pain, generalized malaise, and shortness of breath. In some but not all cases, factors predisposing to ketoacidosis such as insulin dose reduction, acute febrile illness, reduced caloric intake due to illness or surgery, pancreatic disorders suggesting insulin deficiency (e.g., type 1 diabetes, history of pancreatitis or pancreatic surgery), and alcohol abuse were identified.

Before initiating JARDIANCE, consider factors in the patient history that may predispose to ketoacidosis including pancreatic insulin deficiency from any cause, caloric restriction, and alcohol abuse. In patients treated with JARDIANCE consider monitoring for ketoacidosis and temporarily discontinuing JARDIANCE in clinical situations known to predispose to ketoacidosis (e.g., prolonged fasting due to acute illness or surgery).

5.3 Acute Kidney Injury and Impairment in Renal Function

JARDIANCE causes intravascular volume contraction [see Warnings and Precautions (5.1)] and can cause renal impairment [see Adverse Reactions (6.1)] . There have been postmarketing reports of acute kidney injury, some requiring hospitalization and dialysis, in patients receiving SGLT2 inhibitors, including JARDIANCE; some reports involved patients younger than 65 years of age.

Before initiating JARDIANCE, consider factors that may predispose patients to acute kidney injury including hypovolemia, chronic renal insufficiency, congestive heart failure and concomitant medications (diuretics, ACE inhibitors, ARBs, NSAIDs). Consider temporarily discontinuing JARDIANCE in any setting of reduced oral intake (such as acute illness or fasting) or fluid losses (such as gastrointestinal illness or excessive heat exposure); monitor patients for signs and symptoms of acute kidney injury. If acute kidney injury occurs, discontinue JARDIANCE promptly and institute treatment.

JARDIANCE increases serum creatinine and decreases eGFR. Patients with hypovolemia may be more susceptible to these changes. Renal function abnormalities can occur after initiating JARDIANCE [see Adverse Reactions (6.1)] . Renal function should be evaluated prior to initiation of JARDIANCE and monitored periodically thereafter. More frequent renal function monitoring is recommended in patients with an eGFR below 60 mL/min/1.73 m^2. Use of JARDIANCE is not recommended when eGFR is persistently less than 45 mL/min/1.73 m^2and is contraindicated in patients with an eGFR less than 30 mL/min/1.73 m^2 [see Dosage and Administration (2.2), Contraindications (4) and Use in Specific Populations (8.6)] .

5.4 Urosepsis and Pyelonephritis

There have been postmarketing reports of serious urinary tract infections including urosepsis and pyelonephritis requiring hospitalization in patients receiving SGLT2 inhibitors, including JARDIANCE. Treatment with SGLT2 inhibitors increases the risk for urinary tract infections. Evaluate patients for signs and symptoms of urinary tract infections and treat promptly, if indicated [see Adverse Reactions (6)] .

5.5 Hypoglycemia with Concomitant Use with Insulin and Insulin Secretagogues

Insulin and insulin secretagogues are known to cause hypoglycemia. The risk of hypoglycemia is increased when JARDIANCE is used in combination with insulin secretagogues (e.g., sulfonylurea) or insulin [see Adverse Reactions (6.1)] . Therefore, a lower dose of the insulin secretagogue or insulin may be required to reduce the risk of hypoglycemia when used in combination with JARDIANCE.

5.6 Genital Mycotic Infections

JARDIANCE increases the risk for genital mycotic infections [see Adverse Reactions (6.1)] . Patients with a history of chronic or recurrent genital mycotic infections were more likely to develop genital mycotic infections. Monitor and treat as appropriate.

5.7 Hypersensitivity Reactions

There have been postmarketing reports of serious hypersensitivity reactions, (e.g., angioedema) in patients treated with JARDIANCE. If a hypersensitivity reaction occurs, discontinue JARDIANCE; treat promptly per standard of care, and monitor until signs and symptoms resolve. JARDIANCE is contraindicated in patients with a previous serious hypersensitivity reaction to empagliflozin or any of the excipients in JARDIANCE [see Contraindications (4)] .

5.8 Increased Low-Density Lipoprotein Cholesterol (LDL-C)

Increases in LDL-C can occur with JARDIANCE [see Adverse Reactions (6.1)] . Monitor and treat as appropriate.

6 ADVERSE REACTIONS

The following important adverse reactions are described below and elsewhere in the labeling:

- Hypotension [see Warnings and Precautions (5.1)]
- Ketoacidosis [see Warnings and Precautions (5.2)]
- Acute Kidney Injury and Impairment in Renal Function [see Warnings and Precautions (5.3)]
- Urosepsis and Pyelonephritis [see Warnings and Precautions (5.4)]
- Hypoglycemia with Concomitant Use with Insulin and Insulin Secretagogues [see Warnings and Precautions (5.5)]
- Genital Mycotic Infections [see Warnings and Precautions (5.6)]
- Hypersensitivity Reactions [see Warnings and Precautions (5.7)]
- Increased Low-Density Lipoprotein Cholesterol (LDL-C) [see Warnings and Precautions (5.8)]

6.1 Clinical Trials Experience

Because clinical trials are conducted under widely varying conditions, adverse reaction rates observed in the clinical trials of a drug cannot be directly compared to rates in the clinical trials of another drug and may not reflect the rates observed in practice.

Pool of Placebo-Controlled Trials evaluating JARDIANCE 10 and 25 mg
The data in Table 1 are derived from a pool of four 24-week placebo-controlled trials and 18-week data from a placebo-controlled trial with insulin. JARDIANCE was used as monotherapy in one trial and as add-on therapy in four trials [see Clinical Studies (14)] .

These data reflect exposure of 1976 patients to JARDIANCE with a mean exposure duration of approximately 23 weeks. Patients received placebo (N=995), JARDIANCE 10 mg (N=999), or JARDIANCE 25 mg (N=977) once daily. The mean age of the population was 56 years and 3% were older than 75 years of age. More than half (55%) of the population was male; 46% were White, 50% were Asian, and 3% were Black or African American. At baseline, 57% of the population had diabetes more than 5 years and had a mean hemoglobin A1c (HbA1c) of 8%. Established microvascular complications of diabetes at baseline included diabetic nephropathy (7%), retinopathy (8%), or neuropathy (16%). Baseline renal function was normal or mildly impaired in 91% of patients and moderately impaired in 9% of patients (mean eGFR 86.8 mL/min/1.73 m^2).

Table 1 shows common adverse reactions (excluding hypoglycemia) associated with the use of JARDIANCE. The adverse reactions were not present at baseline, occurred more commonly on JARDIANCE than on placebo and occurred in greater than or equal to 2% of patients treated with JARDIANCE 10 mg or JARDIANCE 25 mg.

Table 1 Adverse Reactions Reported in ≥2% of Patients Treated with JARDIANCE and Greater than Placebo in Pooled Placebo-Controlled Clinical Studies of JARDIANCE Monotherapy or Combination Therapy
 | Number (%) of Patients
 | Placebo N=995 | JARDIANCE 10 mg N=999 | JARDIANCE 25 mg N=977
Urinary tract infectiona | 7.6% | 9.3% | 7.6%
Female genital mycotic infectionsb | 1.5% | 5.4% | 6.4%
Upper respiratory tract infection | 3.8% | 3.1% | 4.0%
Increased urinationc | 1.0% | 3.4% | 3.2%
Dyslipidemia | 3.4% | 3.9% | 2.9%
Arthralgia | 2.2% | 2.4% | 2.3%
Male genital mycotic infectionsd | 0.4% | 3.1% | 1.6%
Nausea | 1.4% | 2.3% | 1.1%
aPredefined adverse event grouping, including, but not limited to, urinary tract infection, asymptomatic bacteriuria, cystitis
bFemale genital mycotic infections include the following adverse reactions: vulvovaginal mycotic infection, vaginal infection, vulvitis, vulvovaginal candidiasis, genital infection, genital candidiasis, genital infection fungal, genitourinary tract infection, vulvovaginitis, cervicitis, urogenital infection fungal, vaginitis bacterial. Percentages calculated with the number of female subjects in each group as denominator: placebo (N=481), JARDIANCE 10 mg (N=443), JARDIANCE 25 mg (N=420).
cPredefined adverse event grouping, including, but not limited to, polyuria, pollakiuria, and nocturia
dMale genital mycotic infections include the following adverse reactions: balanoposthitis, balanitis, genital infections fungal, genitourinary tract infection, balanitis candida, scrotal abscess, penile infection. Percentages calculated with the number of male subjects in each group as denominator: placebo (N=514), JARDIANCE 10 mg (N=556), JARDIANCE 25 mg (N=557).

Thirst (including polydipsia) was reported in 0%, 1.7%, and 1.5% for placebo, JARDIANCE 10 mg, and JARDIANCE 25 mg, respectively.

Volume Depletion
JARDIANCE causes an osmotic diuresis, which may lead to intravascular volume contraction and adverse reactions related to volume depletion. In the pool of five placebo-controlled clinical trials, adverse reactions related to volume depletion (e.g., blood pressure (ambulatory) decreased, blood pressure systolic decreased, dehydration, hypotension, hypovolemia, orthostatic hypotension, and syncope) were reported by 0.3%, 0.5%, and 0.3% of patients treated with placebo, JARDIANCE 10 mg, and JARDIANCE 25 mg, respectively. JARDIANCE may increase the risk of hypotension in patients at risk for volume contraction [see Warnings and Precautions (5.1) and Use in Specific Populations (8.5, 8.6)].

Increased Urination
In the pool of five placebo-controlled clinical trials, adverse reactions of increased urination (e.g., polyuria, pollakiuria, and nocturia) occurred more frequently on JARDIANCE than on placebo (see Table 1). Specifically, nocturia was reported by 0.4%, 0.3%, and 0.8% of patients treated with placebo, JARDIANCE 10 mg, and JARDIANCE 25 mg, respectively.

Acute Impairment in Renal Function
Treatment with JARDIANCE was associated with increases in serum creatinine and decreases in eGFR (see Table 2). Patients with moderate renal impairment at baseline had larger mean changes [see Warnings and Precautions (5.3) and Use in Specific Populations (8.5,8.6)] .

In a long-term cardiovascular outcome trial, the acute impairment in renal function was observed to reverse after treatment discontinuation suggesting acute hemodynamic changes play a role in the renal function changes observed with empagliflozin.

Table 2 Changes from Baseline in Serum Creatinine and eGFRain the Pool of Four 24-week Placebo-Controlled Studies and Renal Impairment Study
 |  | Pool of 24-Week Placebo-Controlled Studies
 |  | Placebo | JARDIANCE 10 mg | JARDIANCE 25 mg
Baseline Mean | N | 825 | 830 | 822
Baseline Mean | Creatinine (mg/dL) | 0.84 | 0.85 | 0.85
Baseline Mean | eGFR (mL/min/1.73 m^2) | 87.3 | 87.1 | 87.8
Week 12 Change | N | 771 | 797 | 783
Week 12 Change | Creatinine (mg/dL) | 0.00 | 0.02 | 0.01
Week 12 Change | eGFR (mL/min/1.73 m^2) | -0.3 | -1.3 | -1.4
Week 24 Change | N | 708 | 769 | 754
Week 24 Change | Creatinine (mg/dL) | 0.00 | 0.01 | 0.01
Week 24 Change | eGFR (mL/min/1.73 m^2) | -0.3 | -0.6 | -1.4
 |  | Moderate Renal Impairmentb
 |  | Placebo |  | JARDIANCE 25 mg
Baseline Mean | N | 187 | -- | 187
Baseline Mean | Creatinine (mg/dL) | 1.49 | -- | 1.46
Baseline Mean | eGFR (mL/min/1.73 m^2) | 44.3 | -- | 45.4
Week 12 Change | N | 176 | -- | 179
Week 12 Change | Creatinine (mg/dL) | 0.01 | -- | 0.12
Week 12 Change | eGFR (mL/min/1.73 m^2) | 0.1 | -- | -3.8
Week 24 Change | N | 170 | -- | 171
Week 24 Change | Creatinine (mg/dL) | 0.01 | -- | 0.10
Week 24 Change | eGFR (mL/min/1.73 m^2) | 0.2 | -- | -3.2
Week 52 Change | N | 164 | -- | 162
Week 52 Change | Creatinine (mg/dL) | 0.02 | -- | 0.11
Week 52 Change | eGFR (mL/min/1.73 m^2) | -0.3 | -- | -2.8
Post-treatment Changec | N | 98 | -- | 103
Post-treatment Changec | Creatinine (mg/dL) | 0.03 | -- | 0.02
Post-treatment Changec | eGFR (mL/min/1.73 m^2) | 0.16 | -- | 1.48
aObserved cases on treatment.
bSubset of patients from renal impairment study with eGFR 30 to less than 60 mL/min/1.73 m^2
cApproximately 3 weeks after end of treatment.

Hypoglycemia
The incidence of hypoglycemia by study is shown in Table 3. The incidence of hypoglycemia increased when JARDIANCE was administered with insulin or sulfonylurea [see Warnings and Precautions (5.5)] .

Table 3 Incidence of Overallaand SeverebHypoglycemic Events in Placebo-Controlled Clinical Studiesc
Monotherapy (24 weeks) | Placebo (n=229) | JARDIANCE 10 mg (n=224) | JARDIANCE 25 mg (n=223)
Overall (%) | 0.4% | 0.4% | 0.4%
Severe (%) | 0% | 0% | 0%
In Combination with Metformin (24 weeks) | Placebo + Metformin (n=206) | JARDIANCE 10 mg + Metformin (n=217) | JARDIANCE 25 mg + Metformin (n=214)
Overall (%) | 0.5% | 1.8% | 1.4%
Severe (%) | 0% | 0% | 0%
In Combination with Metformin + Sulfonylurea (24 weeks) | Placebo (n=225) | JARDIANCE 10 mg + Metformin + Sulfonylurea (n=224) | JARDIANCE 25 mg + Metformin + Sulfonylurea (n=217)
Overall (%) | 8.4% | 16.1% | 11.5%
Severe (%) | 0% | 0% | 0%
In Combination with Pioglitazone +/- Metformin (24 weeks) | Placebo (n=165) | JARDIANCE 10 mg + Pioglitazone +/- Metformin (n=165) | JARDIANCE 25 mg + Pioglitazone +/- Metformin (n=168)
Overall (%) | 1.8% | 1.2% | 2.4%
Severe (%) | 0% | 0% | 0%
In Combination with Basal Insulin+/- Metformin (18 weeksd) | Placebo (n=170) | JARDIANCE 10 mg (n=169) | JARDIANCE 25 mg (n=155)
Overall (%) | 20.6% | 19.5% | 28.4%
Severe (%) | 0% | 0% | 1.3%
In Combination with MDI Insulin +/-Metformin (18 weeksd) | Placebo (n=188) | JARDIANCE 10 mg (n=186) | JARDIANCE 25 mg (n=189)
Overall (%) | 37.2% | 39.8% | 41.3%
Severe (%) | 0.5% | 0.5% | 0.5%
aOverall hypoglycemic events: plasma or capillary glucose of less than or equal to 70 mg/dL
bSevere hypoglycemic events: requiring assistance regardless of blood glucose
cTreated set (patients who had received at least one dose of study drug)
dInsulin dose could not be adjusted during the initial 18 week treatment period

Genital Mycotic Infections
In the pool of five placebo-controlled clinical trials, the incidence of genital mycotic infections (e.g., vaginal mycotic infection, vaginal infection, genital infection fungal, vulvovaginal candidiasis, and vulvitis) was increased in patients treated with JARDIANCE compared to placebo, occurring in 0.9%, 4.1%, and 3.7% of patients randomized to placebo, JARDIANCE 10 mg, and JARDIANCE 25 mg, respectively. Discontinuation from study due to genital infection occurred in 0% of placebo-treated patients and 0.2% of patients treated with either JARDIANCE 10 or 25 mg.

Genital mycotic infections occurred more frequently in female than male patients (see Table 1).

Phimosis occurred more frequently in male patients treated with JARDIANCE 10 mg (less than 0.1%) and JARDIANCE 25 mg (0.1%) than placebo (0%).

Urinary Tract Infections
In the pool of five placebo-controlled clinical trials, the incidence of urinary tract infections (e.g., urinary tract infection, asymptomatic bacteriuria, and cystitis) was increased in patients treated with JARDIANCE compared to placebo (see Table 1). Patients with a history of chronic or recurrent urinary tract infections were more likely to experience a urinary tract infection. The rate of treatment discontinuation due to urinary tract infections was 0.1%, 0.2%, and 0.1% for placebo, JARDIANCE 10 mg, and JARDIANCE 25 mg, respectively.

Urinary tract infections occurred more frequently in female patients. The incidence of urinary tract infections in female patients randomized to placebo, JARDIANCE 10 mg, and JARDIANCE 25 mg was 16.6%, 18.4%, and 17.0%, respectively. The incidence of urinary tract infections in male patients randomized to placebo, JARDIANCE 10 mg, and JARDIANCE 25 mg was 3.2%, 3.6%, and 4.1%, respectively [see Warnings and Precautions (5.4) and Use in Specific Populations (8.5)] .

Laboratory Tests
Increase in Low-Density Lipoprotein Cholesterol (LDL-C)
Dose-related increases in low-density lipoprotein cholesterol (LDL-C) were observed in patients treated with JARDIANCE. LDL-C increased by 2.3%, 4.6%, and 6.5% in patients treated with placebo, JARDIANCE 10 mg, and JARDIANCE 25 mg, respectively [see Warnings and Precautions (5.8)] . The range of mean baseline LDL-C levels was 90.3 to 90.6 mg/dL across treatment groups.

Increase in Hematocrit
In a pool of four placebo-controlled studies, median hematocrit decreased by 1.3% in placebo and increased by 2.8% in JARDIANCE 10 mg and 2.8% in JARDIANCE 25 mg treated patients. At the end of treatment, 0.6%, 2.7%, and 3.5% of patients with hematocrits initially within the reference range had values above the upper limit of the reference range with placebo, JARDIANCE 10 mg, and JARDIANCE 25 mg, respectively.

6.2 Postmarketing Experience

Additional adverse reactions have been identified during postapproval use of JARDIANCE. Because these reactions are reported voluntarily from a population of uncertain size, it is generally not possible to reliably estimate their frequency or establish a causal relationship to drug exposure.

- Ketoacidosis [see Warnings and Precautions (5.2)]
- Urosepsis and pyelonephritis [see Warnings and Precautions (5.4)]
- Angioedema [see Warnings and Precautions (5.7)]
- Skin reactions (e.g., rash, urticaria)

7 DRUG INTERACTIONS

7.1 Diuretics

Coadministration of empagliflozin with diuretics resulted in increased urine volume and frequency of voids, which might enhance the potential for volume depletion [see Warnings and Precautions (5.1)] .

7.2 Insulin or Insulin Secretagogues

Coadministration of empagliflozin with insulin or insulin secretagogues increases the risk for hypoglycemia [see Warnings and Precautions (5.5)].

7.3 Positive Urine Glucose Test

Monitoring glycemic control with urine glucose tests is not recommended in patients taking SGLT2 inhibitors as SGLT2 inhibitors increase urinary glucose excretion and will lead to positive urine glucose tests. Use alternative methods to monitor glycemic control.

7.4 Interference with 1,5-anhydroglucitol (1,5-AG) Assay

Monitoring glycemic control with 1,5-AG assay is not recommended as measurements of 1,5-AG are unreliable in assessing glycemic control in patients taking SGLT2 inhibitors. Use alternative methods to monitor glycemic control.

8 USE IN SPECIFIC POPULATIONS

8.1 Pregnancy

Risk Summary
Based on animal data showing adverse renal effects, JARDIANCE is not recommended during the second and third trimesters of pregnancy.

Limited data available with JARDIANCE in pregnant women are not sufficient to determine a drug-associated risk for major birth defects and miscarriage. There are risks to the mother and fetus associated with poorly controlled diabetes in pregnancy [see Clinical Considerations] .

In animal studies, adverse renal changes were observed in rats when empagliflozin was administered during a period of renal development corresponding to the late second and third trimesters of human pregnancy. Doses approximately 13-times the maximum clinical dose caused renal pelvic and tubule dilatations that were reversible. Empagliflozin was not teratogenic in rats and rabbits up to 300 mg/kg/day, which approximates 48-times and 128-times, respectively, the maximum clinical dose of 25 mg when administered during organogenesis [see Data] .

The estimated background risk of major birth defects is 6-10% in women with pre-gestational diabetes with a HbA1c >7 and has been reported to be as high as 20-25% in women with HbA1c >10. The estimated background risk of miscarriage for the indicated population is unknown. In the U.S. general population, the estimated background risk of major birth defects and miscarriage in clinically recognized pregnancies is 2-4% and 15-20%, respectively.

Clinical Considerations
Disease-associated maternal and/or embryo/fetal risk:Poorly controlled diabetes in pregnancy increases the maternal risk for diabetic ketoacidosis, pre-eclampsia, spontaneous abortions, preterm delivery, stillbirth, and delivery complications. Poorly controlled diabetes increases the fetal risk for major birth defects, stillbirth, and macrosomia related morbidity.

Data
Animal Data
Empagliflozin dosed directly to juvenile rats from postnatal day (PND) 21 until PND 90 at doses of 1, 10, 30 and 100 mg/kg/day caused increased kidney weights and renal tubular and pelvic dilatation at 100 mg/kg/day, which approximates 13-times the maximum clinical dose of 25 mg, based on AUC. These findings were not observed after a 13 week drug-free recovery period. These outcomes occurred with drug exposure during periods of renal development in rats that correspond to the late second and third trimester of human renal development.

In embryo-fetal development studies in rats and rabbits, empagliflozin was administered for intervals coinciding with the first trimester period of organogenesis in humans. Doses up to 300 mg/kg/day, which approximates 48-times (rats) and 128-times (rabbits) the maximum clinical dose of 25 mg (based on AUC), did not result in adverse developmental effects. In rats, at higher doses of empagliflozin causing maternal toxicity, malformations of limb bones increased in fetuses at 700 mg/kg/day or 154-times the 25 mg maximum clinical dose. Empagliflozin crosses the placenta and reaches fetal tissues in rats. In the rabbit, higher doses of empagliflozin resulted in maternal and fetal toxicity at 700 mg/kg/day, or 139-times the 25 mg maximum clinical dose.

In pre- and postnatal development studies in pregnant rats, empagliflozin was administered from gestation day 6 through to lactation day 20 (weaning) at up to 100 mg/kg/day (approximately 16 times the 25 mg maximum clinical dose) without maternal toxicity. Reduced body weight was observed in the offspring at greater than or equal to 30 mg/kg/day (approximately 4 times the 25 mg maximum clinical dose).

8.2 Lactation

Risk Summary
There is no information regarding the presence of JARDIANCE in human milk, the effects of JARDIANCE on the breastfed infant or the effects on milk production. Empagliflozin is present in the milk of lactating rats [see Data] . Since human kidney maturation occurs in uteroand during the first 2 years of life when lactational exposure may occur, there may be risk to the developing human kidney.

Because of the potential for serious adverse reactions in a breastfed infant, including the potential for empagliflozin to affect postnatal renal development, advise women that use of JARDIANCE is not recommended while breastfeeding.

Data
Empagliflozin was present at a low level in rat fetal tissues after a single oral dose to the dams at gestation day 18. In rat milk, the mean milk to plasma ratio ranged from 0.634 -5, and was greater than one from 2 to 24 hours post-dose. The mean maximal milk to plasma ratio of 5 occurred at 8 hours post-dose, suggesting accumulation of empagliflozin in the milk. Juvenile rats directly exposed to empagliflozin showed a risk to the developing kidney (renal pelvic and tubular dilatations) during maturation.

8.4 Pediatric Use

The safety and effectiveness of JARDIANCE in pediatric patients under 18 years of age have not been established.

8.5 Geriatric Use

No JARDIANCE dosage change is recommended based on age [see Dosage and Administration (2)] . In studies assessing the efficacy of empagliflozin in improving glycemic control in patients with type 2 diabetes, a total of 2721 (32%) patients treated with empagliflozin were 65 years of age and older, and 491 (6%) were 75 years of age and older. JARDIANCE is expected to have diminished glycemic efficacy in elderly patients with renal impairment [see Use in Specific Populations (8.6)] . The risk of volume depletion-related adverse reactions increased in patients who were 75 years of age and older to 2.1%, 2.3%, and 4.4% for placebo, JARDIANCE 10 mg, and JARDIANCE 25 mg. The risk of urinary tract infections increased in patients who were 75 years of age and older to 10.5%, 15.7%, and 15.1% in patients randomized to placebo, JARDIANCE 10 mg, and JARDIANCE 25 mg, respectively [see Warnings and Precautions (5.1) and Adverse Reactions (6.1)] .

8.6 Renal Impairment

The efficacy and safety of JARDIANCE were evaluated in a study of patients with mild and moderate renal impairment [see Clinical Studies (14.1)] . In this study, 195 patients exposed to JARDIANCE had an eGFR between 60 and 90 mL/min/1.73 m^2, 91 patients exposed to JARDIANCE had an eGFR between 45 and 60 mL/min/1.73 m^2and 97 patients exposed to JARDIANCE had an eGFR between 30 and 45 mL/min/1.73 m^2. The glucose lowering benefit of JARDIANCE 25 mg decreased in patients with worsening renal function. The risks of renal impairment [see Warnings and Precautions (5.3)] , volume depletion adverse reactions and urinary tract infection-related adverse reactions increased with worsening renal function.

In a large cardiovascular outcomes study, there were 1819 patients with eGFR below 60 mL/min/1.73 m^2. The cardiovascular death findings in this subgroup were consistent with the overall findings [see Clinical Studies (14.2)].

The efficacy and safety of JARDIANCE have not been established in patients with severe renal impairment, with ESRD, or receiving dialysis. JARDIANCE is not expected to be effective in these patient populations [see Dosage and Administration (2.2), Contraindications (4) and Warnings and Precautions (5.1,5.3)].

8.7 Hepatic Impairment

JARDIANCE may be used in patients with hepatic impairment [see Clinical Pharmacology (12.3)] .

10 OVERDOSAGE

In the event of an overdose with JARDIANCE, contact the Poison Control Center. Employ the usual supportive measures (e.g., remove unabsorbed material from the gastrointestinal tract, employ clinical monitoring, and institute supportive treatment) as dictated by the patient’s clinical status. Removal of empagliflozin by hemodialysis has not been studied.

11 DESCRIPTION

JARDIANCE tablets contain empagliflozin, an orally-active inhibitor of the sodium-glucose co-transporter 2 (SGLT2).

The chemical name of empagliflozin is D-Glucitol,1,5-anhydro-1-C-[4-chloro-3-[[4-[[(3S)-tetrahydro-3-furanyl]oxy]phenyl]methyl]phenyl]-, (1S).

Its molecular formula is C23H27ClO7and the molecular weight is 450.91. The structural formula is:

Empagliflozin is a white to yellowish, non-hygroscopic powder. It is very slightly soluble in water, sparingly soluble in methanol, slightly soluble in ethanol and acetonitrile; soluble in 50% acetonitrile/water; and practically insoluble in toluene.

Each film-coated tablet of JARDIANCE contains 10 mg or 25 mg of empagliflozin (free base) and the following inactive ingredients: lactose monohydrate, microcrystalline cellulose, hydroxypropyl cellulose, croscarmellose sodium, colloidal silicon dioxide and magnesium stearate. In addition, the film coating contains the following inactive ingredients: hypromellose, titanium dioxide, talc, polyethylene glycol, and yellow ferric oxide.

12 CLINICAL PHARMACOLOGY

12.1 Mechanism of Action

Sodium-glucose co-transporter 2 (SGLT2) is the predominant transporter responsible for reabsorption of glucose from the glomerular filtrate back into the circulation. Empagliflozin is an inhibitor of SGLT2. By inhibiting SGLT2, empagliflozin reduces renal reabsorption of filtered glucose and lowers the renal threshold for glucose, and thereby increases urinary glucose excretion.

12.2 Pharmacodynamics

Urinary Glucose Excretion
In patients with type 2 diabetes, urinary glucose excretion increased immediately following a dose of JARDIANCE and was maintained at the end of a 4-week treatment period averaging at approximately 64 grams per day with 10 mg empagliflozin and 78 grams per day with 25 mg JARDIANCE once daily [see Clinical Studies (14)].

Urinary Volume
In a 5-day study, mean 24-hour urine volume increase from baseline was 341 mL on Day 1 and 135 mL on Day 5 of empagliflozin 25 mg once daily treatment.

Cardiac Electrophysiology
In a randomized, placebo-controlled, active-comparator, crossover study, 30 healthy subjects were administered a single oral dose of JARDIANCE 25 mg, JARDIANCE 200 mg (8 times the maximum dose), moxifloxacin, and placebo. No increase in QTc was observed with either 25 mg or 200 mg empagliflozin.

12.3 Pharmacokinetics

Absorption
The pharmacokinetics of empagliflozin has been characterized in healthy volunteers and patients with type 2 diabetes and no clinically relevant differences were noted between the two populations. After oral administration, peak plasma concentrations of empagliflozin were reached at 1.5 hours post-dose. Thereafter, plasma concentrations declined in a biphasic manner with a rapid distribution phase and a relatively slow terminal phase. The steady state mean plasma AUC and Cmaxwere 1870 nmol·h/L and 259 nmol/L, respectively, with 10 mg empagliflozin once daily treatment, and 4740 nmol·h/L and 687 nmol/L, respectively, with 25 mg empagliflozin once daily treatment. Systemic exposure of empagliflozin increased in a dose-proportional manner in the therapeutic dose range. The single-dose and steady-state pharmacokinetic parameters of empagliflozin were similar, suggesting linear pharmacokinetics with respect to time.

Administration of 25 mg empagliflozin after intake of a high-fat and high-calorie meal resulted in slightly lower exposure; AUC decreased by approximately 16% and Cmaxdecreased by approximately 37%, compared to fasted condition. The observed effect of food on empagliflozin pharmacokinetics was not considered clinically relevant and empagliflozin may be administered with or without food.

Distribution
The apparent steady-state volume of distribution was estimated to be 73.8 L based on a population pharmacokinetic analysis. Following administration of an oral [^14C]-empagliflozin solution to healthy subjects, the red blood cell partitioning was approximately 36.8% and plasma protein binding was 86.2%.

Metabolism
No major metabolites of empagliflozin were detected in human plasma and the most abundant metabolites were three glucuronide conjugates (2-O-, 3-O-, and 6-O-glucuronide). Systemic exposure of each metabolite was less than 10% of total drug-related material. In vitrostudies suggested that the primary route of metabolism of empagliflozin in humans is glucuronidation by the uridine 5'-diphospho-glucuronosyltransferases UGT2B7, UGT1A3, UGT1A8, and UGT1A9.

Elimination
The apparent terminal elimination half-life of empagliflozin was estimated to be 12.4 h and apparent oral clearance was 10.6 L/h based on the population pharmacokinetic analysis. Following once-daily dosing, up to 22% accumulation, with respect to plasma AUC, was observed at steady-state, which was consistent with empagliflozin half-life. Following administration of an oral [^14C]-empagliflozin solution to healthy subjects, approximately 95.6% of the drug-related radioactivity was eliminated in feces (41.2%) or urine (54.4%). The majority of drug-related radioactivity recovered in feces was unchanged parent drug and approximately half of drug-related radioactivity excreted in urine was unchanged parent drug.

Specific Populations
Renal Impairment
In patients with mild (eGFR: 60 to less than 90 mL/min/1.73 m^2), moderate (eGFR: 30 to less than 60 mL/min/1.73 m^2), and severe (eGFR: less than 30 mL/min/1.73 m^2) renal impairment and subjects with kidney failure/end stage renal disease (ESRD) patients, AUC of empagliflozin increased by approximately 18%, 20%, 66%, and 48%, respectively, compared to subjects with normal renal function. Peak plasma levels of empagliflozin were similar in subjects with moderate renal impairment and kidney failure/ESRD compared to patients with normal renal function. Peak plasma levels of empagliflozin were roughly 20% higher in subjects with mild and severe renal impairment as compared to subjects with normal renal function. Population pharmacokinetic analysis showed that the apparent oral clearance of empagliflozin decreased, with a decrease in eGFR leading to an increase in drug exposure. However, the fraction of empagliflozin that was excreted unchanged in urine, and urinary glucose excretion, declined with decrease in eGFR.

Hepatic Impairment
In subjects with mild, moderate, and severe hepatic impairment according to the Child-Pugh classification, AUC of empagliflozin increased by approximately 23%, 47%, and 75%, and Cmaxincreased by approximately 4%, 23%, and 48%, respectively, compared to subjects with normal hepatic function.

Effects of Age, Body Mass Index, Gender, and Race
Based on the population PK analysis, age, body mass index (BMI), gender and race (Asians versus primarily Whites) do not have a clinically meaningful effect on pharmacokinetics of empagliflozin [see Use in Specific Populations (8.5)] .

Pediatric
Studies characterizing the pharmacokinetics of empagliflozin in pediatric patients have not been performed.

Drug Interactions
In vitroAssessment of Drug Interactions
Empagliflozin does not inhibit, inactivate, or induce CYP450 isoforms. In vitrodata suggest that the primary route of metabolism of empagliflozin in humans is glucuronidation by the uridine 5'-diphospho-glucuronosyltransferases UGT1A3, UGT1A8, UGT1A9, and UGT2B7. Empagliflozin does not inhibit UGT1A1, UGT1A3, UGT1A8, UGT1A9, or UGT2B7. Therefore, no effect of empagliflozin is anticipated on concomitantly administered drugs that are substrates of the major CYP450 isoforms or UGT1A1, UGT1A3, UGT1A8, UGT1A9, or UGT2B7. The effect of UGT induction (e.g., induction by rifampicin or any other UGT enzyme inducer) on empagliflozin exposure has not been evaluated.

Empagliflozin is a substrate for P-glycoprotein (P-gp) and breast cancer resistance protein (BCRP), but it does not inhibit these efflux transporters at therapeutic doses. Based on in vitrostudies, empagliflozin is considered unlikely to cause interactions with drugs that are P-gp substrates. Empagliflozin is a substrate of the human uptake transporters OAT3, OATP1B1, and OATP1B3, but not OAT1 and OCT2. Empagliflozin does not inhibit any of these human uptake transporters at clinically relevant plasma concentrations and, therefore, no effect of empagliflozin is anticipated on concomitantly administered drugs that are substrates of these uptake transporters.

In vivoAssessment of Drug Interactions
No dose adjustment of JARDIANCE is recommended when coadministered with commonly prescribed medicinal products based on results of the described pharmacokinetic studies. Empagliflozin pharmacokinetics were similar with and without coadministration of metformin, glimepiride, pioglitazone, sitagliptin, linagliptin, warfarin, verapamil, ramipril, and simvastatin in healthy volunteers and with or without coadministration of hydrochlorothiazide and torsemide in patients with type 2 diabetes (see Figure 1). The observed increases in overall exposure (AUC) of empagliflozin following coadministration with gemfibrozil, rifampicin, or probenecid are not clinically relevant. In subjects with normal renal function, coadministration of empagliflozin with probenecid resulted in a 30% decrease in the fraction of empagliflozin excreted in urine without any effect on 24-hour urinary glucose excretion. The relevance of this observation to patients with renal impairment is unknown.

Figure 1 Effect of Various Medications on the Pharmacokinetics of Empagliflozin as Displayed as 90% Confidence Interval of Geometric Mean AUC and CmaxRatios [reference lines indicate 100% (80% - 125%)]

aempagliflozin, 50 mg, once daily;bempagliflozin, 25 mg, single dose;cempagliflozin, 25 mg, once daily;dempagliflozin, 10 mg, single dose

Empagliflozin had no clinically relevant effect on the pharmacokinetics of metformin, glimepiride, pioglitazone, sitagliptin, linagliptin, warfarin, digoxin, ramipril, simvastatin, hydrochlorothiazide, torsemide, and oral contraceptives when coadministered in healthy volunteers (see Figure 2).

Figure 2 Effect of Empagliflozin on the Pharmacokinetics of Various Medications as Displayed as 90% Confidence Interval of Geometric Mean AUC and CmaxRatios [reference lines indicate 100% (80% - 125%)]

aempagliflozin, 50 mg, once daily;bempagliflozin, 25 mg, once daily;cempagliflozin, 25 mg, single dose;dadministered as simvastatin;eadministered as warfarin racemic mixture;fadministered as Microgynon®;gadministered as ramipril

13 NONCLINICAL TOXICOLOGY

13.1 Carcinogenesis, Mutagenesis, Impairment of Fertility

Carcinogenesis
Carcinogenesis was evaluated in 2-year studies conducted in CD-1 mice and Wistar rats. Empagliflozin did not increase the incidence of tumors in female rats dosed at 100, 300, or 700 mg/kg/day (up to 72 times the exposure from the maximum clinical dose of 25 mg). In male rats, hemangiomas of the mesenteric lymph node were increased significantly at 700 mg/kg/day or approximately 42 times the exposure from a 25 mg clinical dose. Empagliflozin did not increase the incidence of tumors in female mice dosed at 100, 300, or 1000 mg/kg/day (up to 62 times the exposure from a 25 mg clinical dose). Renal tubule adenomas and carcinomas were observed in male mice at 1000 mg/kg/day, which is approximately 45 times the exposure of the maximum clinical dose of 25 mg. These tumors may be associated with a metabolic pathway predominantly present in the male mouse kidney.

Mutagenesis
Empagliflozin was not mutagenic or clastogenic with or without metabolic activation in the in vitroAmes bacterial mutagenicity assay, the in vitroL5178Y tk+/-mouse lymphoma cell assay, and an in vivomicronucleus assay in rats.

Impairment of Fertility
Empagliflozin had no effects on mating, fertility or early embryonic development in treated male or female rats up to the high dose of 700 mg/kg/day (approximately 155 times the 25 mg clinical dose in males and females, respectively).

14 CLINICAL STUDIES

14.1 Glycemic Control

JARDIANCE has been studied as monotherapy and in combination with metformin, sulfonylurea, pioglitazone, linagliptin, and insulin. JARDIANCE has also been studied in patients with type 2 diabetes with mild or moderate renal impairment.

In patients with type 2 diabetes, treatment with JARDIANCE reduced hemoglobin A1c (HbA1c), compared to placebo. The reduction in HbA1c for JARDIANCE compared with placebo was observed across subgroups including gender, race, geographic region, baseline BMI and duration of disease.

Monotherapy
A total of 986 patients with type 2 diabetes participated in a double-blind, placebo-controlled study to evaluate the efficacy and safety of JARDIANCE monotherapy.

Treatment-naïve patients with inadequately controlled type 2 diabetes entered an open-label placebo run-in for 2 weeks. At the end of the run-in period, patients who remained inadequately controlled and had an HbA1c between 7 and 10% were randomized to placebo, JARDIANCE 10 mg, JARDIANCE 25 mg, or a reference comparator.

At Week 24, treatment with JARDIANCE 10 mg or 25 mg daily provided statistically significant reductions in HbA1c (p-value <0.0001), fasting plasma glucose (FPG), and body weight compared with placebo (see Table 4 and Figure 3).

Table 4 Results at Week 24 From a Placebo-Controlled Monotherapy Study of JARDIANCE
 |  | JARDIANCE 10 mg N=224 | JARDIANCE 25 mg N=224 | Placebo N=228
HbA1c (%)a
 | Baseline (mean) | 7.9 | 7.9 | 7.9
 | Change from baseline (adjusted mean) | -0.7 | -0.8 | 0.1
 | Difference from placebo (adjusted mean) (97.5% CI) | -0.7b(-0.9, -0.6) | -0.9b(-1.0, -0.7) | --
 | Patients [n (%)] achieving HbA1c <7% | 72 (35%) | 88 (44%) | 25 (12%)
FPG (mg/dL)c
 | Baseline (mean) | 153 | 153 | 155
 | Change from baseline (adjusted mean) | -19 | -25 | 12
 | Difference from placebo (adjusted mean) (95% CI) | -31 (-37, -26) | -36 (-42, -31) | --
Body Weight
 | Baseline (mean) in kg | 78 | 78 | 78
 | % change from baseline (adjusted mean) | -2.8 | -3.2 | -0.4
 | Difference from placebo (adjusted mean) (95% CI) | -2.5b(-3.1, -1.9) | -2.8b(-3.4, -2.2) | --
aModified intent to treat population. Last observation on study (LOCF) was used to impute missing data at Week 24. At Week 24, 9.4%, 9.4%, and 30.7% was imputed for patients randomized to JARDIANCE 10 mg, JARDIANCE 25 mg, and placebo, respectively.
bANCOVA derived p-value <0.0001 (HbA1c: ANCOVA model includes baseline HbA1c, treatment, renal function, and region. Body weight and FPG: same model used as for HbA1c but additionally including baseline body weight/baseline FPG, respectively.)
cFPG (mg/dL); for JARDIANCE 10 mg, n=223, for JARDIANCE 25 mg, n=223, and for placebo, n=226

Figure 3 Adjusted Mean HbA1c Change at Each Time Point (Completers) and at Week 24 (mITT Population) - LOCF

At Week 24, the systolic blood pressure was statistically significantly reduced compared to placebo by -2.6 mmHg (placebo-adjusted, p-value=0.0231) in patients randomized to 10 mg of JARDIANCE and by -3.4 mmHg (placebo-corrected, p-value=0.0028) in patients randomized to 25 mg of JARDIANCE.

Add-On Combination Therapy with Metformin
A total of 637 patients with type 2 diabetes participated in a double-blind, placebo-controlled study to evaluate the efficacy and safety of JARDIANCE in combination with metformin.

Patients with type 2 diabetes inadequately controlled on at least 1500 mg of metformin per day entered an open-label 2 week placebo run-in. At the end of the run-in period, patients who remained inadequately controlled and had an HbA1c between 7 and 10% were randomized to placebo, JARDIANCE 10 mg, or JARDIANCE 25 mg.

At Week 24, treatment with JARDIANCE 10 mg or 25 mg daily provided statistically significant reductions in HbA1c (p-value <0.0001), FPG, and body weight compared with placebo (see Table 5).

Table 5 Results at Week 24 From a Placebo-Controlled Study for JARDIANCE used in Combination with Metformin
 |  | JARDIANCE 10 mg + Metformin N=217 | JARDIANCE 25 mg + Metformin N=213 | Placebo + Metformin N=207
HbA1c (%)a
 | Baseline (mean) | 7.9 | 7.9 | 7.9
 | Change from baseline (adjusted mean) | -0.7 | -0.8 | -0.1
 | Difference from placebo + metformin (adjusted mean) (95% CI) | -0.6b(-0.7, -0.4) | -0.6b(-0.8, -0.5) | --
 | Patients [n (%)] achieving HbA1c <7% | 75 (38%) | 74 (39%) | 23 (13%)
FPG (mg/dL)c
 | Baseline (mean) | 155 | 149 | 156
 | Change from baseline (adjusted mean) | -20 | -22 | 6
 | Difference from placebo + metformin (adjusted mean) | -26 | -29 | --
Body Weight
 | Baseline mean in kg | 82 | 82 | 80
 | % change from baseline (adjusted mean) | -2.5 | -2.9 | -0.5
 | Difference from placebo (adjusted mean) (95% CI) | -2.0b(-2.6, -1.4) | -2.5b(-3.1, -1.9) | --
aModified intent to treat population. Last observation on study (LOCF) was used to impute missing data at Week 24. At Week 24, 9.7%, 14.1%, and 24.6% was imputed for patients randomized to JARDIANCE 10 mg, JARDIANCE 25 mg, and placebo, respectively.
bANCOVA p-value <0.0001 (HbA1c: ANCOVA model includes baseline HbA1c, treatment, renal function, and region. Body weight and FPG: same model used as for HbA1c but additionally including baseline body weight/baseline FPG, respectively.)
cFPG (mg/dL); for JARDIANCE 10 mg, n=216, for JARDIANCE 25 mg, n=213, and for placebo, n=207

At Week 24, the systolic blood pressure was statistically significantly reduced compared to placebo by -4.1 mmHg (placebo-corrected, p-value <0.0001) for JARDIANCE 10 mg and -4.8 mmHg (placebo-corrected, p-value <0.0001) for JARDIANCE 25 mg.

Initial Combination Therapy with Metformin
A total of 1364 patients with type 2 diabetes participated in a double-blind, randomized, active-controlled study to evaluate the efficacy and safety of JARDIANCE in combination with metformin as initial therapy compared to the corresponding individual components.

Treatment-naïve patients with inadequately controlled type 2 diabetes entered an open-label placebo run-in for 2 weeks. At the end of the run-in period, patients who remained inadequately controlled and had an HbA1c between 7 and 10.5% were randomized to one of 8 active-treatment arms: JARDIANCE 10 mg or 25 mg; metformin 1000 mg, or 2000 mg; JARDIANCE 10 mg in combination with 1000 mg or 2000 mg metformin; or JARDIANCE 25 mg in combination with 1000 mg or 2000 mg metformin.

At Week 24, initial therapy of JARDIANCE in combination with metformin provided statistically significant reductions in HbA1c (p-value <0.01) compared to the individual components (see Table 6).

Table 6 Glycemic Parameters at 24 Weeks in a Study Comparing JARDIANCE and Metformin to the Individual Components as Initial Therapy
 | JARDIANCE 10 mg + Metformin 1000 mga N=161 | JARDIANCE 10 mg + Metformin 2000 mga N=167 | JARDIANCE 25 mg + Metformin 1000 mga N=165 | JARDIANCE 25 mg + Metformin 2000 mga N=169 | JARDIANCE 10 mg N=169 | JARDIANCE 25 mg N=163 | Metformin 1000 mga N=167 | Metformin 2000 mga N=162
HbA1c (%)
Baseline (mean) | 8.7 | 8.7 | 8.8 | 8.7 | 8.6 | 8.9 | 8.7 | 8.6
Change from baseline (adjusted mean) | -2.0 | -2.1 | -1.9 | -2.1 | -1.4 | -1.4 | -1.2 | -1.8
Comparison vs JARDIANCE (adjusted mean) (95% CI) | -0.6b (-0.9, -0.4) | -0.7b (-1.0, -0.5) | -0.6c (-0.8, -0.3) | -0.7c (-1.0, -0.5) | -- | -- | -- | --
Comparison vs metformin (adjusted mean) (95% CI) | -0.8b (-1.0, -0.6) | -0.3b (-0.6, -0.1) | -0.8c (-1.0, -0.5) | -0.3c (-0.6, -0.1) | -- | -- | -- | --
aMetformin total daily dose, administered in two equally divided doses per day.
bp-value ≤0.0062 (modified intent to treat population [observed case] MMRM model included treatment, renal function, region, visit, visit by treatment interaction, and baseline HbA1c).
cp-value ≤0.0056 (modified intent to treat population [observed case] MMRM model included treatment, renal function, region, visit, visit by treatment interaction, and baseline HbA1c).

Add-On Combination Therapy with Metformin and Sulfonylurea
A total of 666 patients with type 2 diabetes participated in a double-blind, placebo-controlled study to evaluate the efficacy and safety of JARDIANCE in combination with metformin plus a sulfonylurea.

Patients with inadequately controlled type 2 diabetes on at least 1500 mg per day of metformin and on a sulfonylurea, entered a 2 week open-label placebo run-in. At the end of the run-in, patients who remained inadequately controlled and had an HbA1c between 7% and 10% were randomized to placebo, JARDIANCE 10 mg, or JARDIANCE 25 mg.

Treatment with JARDIANCE 10 mg or 25 mg daily provided statistically significant reductions in HbA1c (p-value <0.0001), FPG, and body weight compared with placebo (see Table 7).

Table 7 Results at Week 24 from a Placebo-Controlled Study for JARDIANCE in Combination with Metformin and Sulfonylurea
 |  | JARDIANCE 10 mg + Metformin + SU N=225 | JARDIANCE 25 mg + Metformin + SU N=216 | Placebo + Metformin + SU N=225
HbA1c (%)a
 | Baseline (mean) | 8.1 | 8.1 | 8.2
 | Change from baseline (adjusted mean) | -0.8 | -0.8 | -0.2
 | Difference from placebo (adjusted mean) (95% CI) | -0.6b(-0.8, -0.5) | -0.6b(-0.7, -0.4) | --
 | Patients [n (%)] achieving HbA1c <7% | 55 (26%) | 65 (32%) | 20 (9%)
FPG (mg/dL)c
 | Baseline (mean) | 151 | 156 | 152
 | Change from baseline (adjusted mean) | -23 | -23 | 6
 | Difference from placebo (adjusted mean) | -29 | -29 | --
Body Weight
 | Baseline mean in kg | 77 | 78 | 76
 | % change from baseline (adjusted mean) | -2.9 | -3.2 | -0.5
 | Difference from placebo (adjusted mean) (95% CI) | -2.4b(-3.0, -1.8) | -2.7b(-3.3, -2.1) | --
aModified intent to treat population. Last observation on study (LOCF) was used to impute missing data at Week 24. At Week 24, 17.8%, 16.7%, and 25.3% was imputed for patients randomized to JARDIANCE 10 mg, JARDIANCE 25 mg, and placebo, respectively.
bANCOVA p-value <0.0001 (HbA1c: ANCOVA model includes baseline HbA1c, treatment, renal function, and region. Body weight and FPG: same model used as for HbA1c but additionally including baseline body weight/baseline FPG, respectively.)
cFPG (mg/dL); for JARDIANCE 10 mg, n=225, for JARDIANCE 25 mg, n=215, for placebo, n=224

In Combination with Linagliptin as Add-On to Metformin Therapy
A total of 686 patients with type 2 diabetes participated in a double-blind, active-controlled study to evaluate the efficacy and safety of JARDIANCE 10 mg or 25 mg in combination with linagliptin 5 mg compared to the individual components.

Patients with type 2 diabetes inadequately controlled on at least 1500 mg of metformin per day entered a single-blind placebo run-in period for 2 weeks. At the end of the run-in period, patients who remained inadequately controlled and had an HbA1c between 7 and 10.5% were randomized 1:1:1:1:1 to one of 5 active-treatment arms of JARDIANCE 10 mg or 25 mg, linagliptin 5 mg, or linagliptin 5 mg in combination with 10 mg or 25 mg JARDIANCE as a fixed dose combination tablet.

At Week 24, JARDIANCE 10 mg or 25 mg used in combination with linagliptin 5 mg provided statistically significant improvement in HbA1c (p-value <0.0001) and FPG (p-value <0.001) compared to the individual components in patients who had been inadequately controlled on metformin. Treatment with JARDIANCE/linagliptin 25 mg/5 mg or JARDIANCE/linagliptin 10 mg/5 mg daily also resulted in a statistically significant reduction in body weight compared to linagliptin 5 mg (p-value <0.0001). There was no statistically significant difference in body weight compared to JARDIANCE alone.

Active-Controlled Study versus Glimepiride in Combination with Metformin
The efficacy of JARDIANCE was evaluated in a double-blind, glimepiride-controlled, study in 1545 patients with type 2 diabetes with insufficient glycemic control despite metformin therapy.

Patients with inadequate glycemic control and an HbA1c between 7% and 10% after a 2-week run-in period were randomized to glimepiride or JARDIANCE 25 mg.

At Week 52, JARDIANCE 25 mg and glimepiride lowered HbA1c and FPG (see Table 8, Figure 4). The difference in observed effect size between JARDIANCE 25 mg and glimepiride excluded the pre-specified non-inferiority margin of 0.3%. The mean daily dose of glimepiride was 2.7 mg and the maximal approved dose in the United States is 8 mg per day.

Table 8 Results at Week 52 from an Active-Controlled Study Comparing JARDIANCE to Glimepiride as Add-On Therapy in Patients Inadequately Controlled on Metformin
 |  | JARDIANCE 25 mg + Metformin N=765 | Glimepiride + Metformin N=780
HbA1c (%)a
 | Baseline (mean) | 7.9 | 7.9
 | Change from baseline (adjusted mean) | -0.7 | -0.7
 | Difference from glimepiride (adjusted mean) (97.5% CI) | -0.07b(-0.15, 0.01) | --
FPG (mg/dL)d
 | Baseline (mean) | 150 | 150
 | Change from baseline (adjusted mean) | -19 | -9
 | Difference from glimepiride (adjusted mean) | -11 | --
Body Weight
 | Baseline mean in kg | 82.5 | 83
 | % change from baseline (adjusted mean) | -3.9 | 2.0
 | Difference from glimepiride (adjusted mean) (95% CI) | -5.9c(-6.3, -5.5) | --
aModified intent to treat population. Last observation on study (LOCF) was used to impute data missing at Week 52. At Week 52, data was imputed for 15.3% and 21.9% of patients randomized to JARDIANCE 25 mg and glimepiride, respectively.
bNon-inferior, ANCOVA model p-value <0.0001 (HbA1c: ANCOVA model includes baseline HbA1c, treatment, renal function, and region)
cANCOVA p-value <0.0001 (Body weight and FPG: same model used as for HbA1c but additionally including baseline body weight/baseline FPG, respectively.)
dFPG (mg/dL); for JARDIANCE 25 mg, n=764, for placebo, n=779

Figure 4 Adjusted mean HbA1c Change at Each Time Point (Completers) and at Week 52 (mITT Population) - LOCF

At Week 52, the adjusted mean change from baseline in systolic blood pressure was -3.6 mmHg, compared to 2.2 mmHg for glimepiride. The differences between treatment groups for systolic blood pressure was statistically significant (p-value <0.0001).

At Week 104, the adjusted mean change from baseline in HbA1c was -0.75% for JARDIANCE 25 mg and -0.66% for glimepiride. The adjusted mean treatment difference was -0.09% with a 97.5% confidence interval of (-0.32%, 0.15%), excluding the pre-specified non-inferiority margin of 0.3%. The mean daily dose of glimepiride was 2.7 mg and the maximal approved dose in the United States is 8 mg per day. The Week 104 analysis included data with and without concomitant glycemic rescue medication, as well as off-treatment data. Missing data for patients not providing any information at the visit were imputed based on the observed off-treatment data. In this multiple imputation analysis, 13.9% of the data were imputed for JARDIANCE 25 mg and 12.9% for glimepiride.

At Week 104, JARDIANCE 25 mg daily resulted in a statistically significant difference in change from baseline for body weight compared to glimepiride (-3.1 kg for JARDIANCE 25 mg vs. +1.3 kg for glimepiride; ANCOVA-LOCF, p-value <0.0001).

Add-On Combination Therapy with Pioglitazone with or without Metformin
A total of 498 patients with type 2 diabetes participated in a double-blind, placebo-controlled study to evaluate the efficacy and safety of JARDIANCE in combination with pioglitazone, with or without metformin.

Patients with inadequately controlled type 2 diabetes on metformin at a dose of at least 1500 mg per day and pioglitazone at a dose of at least 30 mg per day were placed into an open-label placebo run-in for 2 weeks. Patients with inadequate glycemic control and an HbA1c between 7% and 10% after the run-in period were randomized to placebo, JARDIANCE 10 mg, or JARDIANCE 25 mg.

Treatment with JARDIANCE 10 mg or 25 mg daily resulted in statistically significant reductions in HbA1c (p-value <0.0001), FPG, and body weight compared with placebo (see Table 9).

Table 9 Results of Placebo-Controlled Study for JARDIANCE in Combination Therapy with Pioglitazone
 |  | JARDIANCE 10 mg + Pioglitazone N=165 | JARDIANCE 25 mg + Pioglitazone N=168 | Placebo + Pioglitazone N=165
HbA1c (%)a
 | Baseline (mean) | 8.1 | 8.1 | 8.2
 | Change from baseline (adjusted mean) | -0.6 | -0.7 | -0.1
 | Difference from placebo + pioglitazone (adjusted mean) (95% CI) | -0.5b(-0.7, -0.3) | -0.6b(-0.8, -0.4) | --
 | Patients [n (%)] achieving HbA1c <7% | 36 (24%) | 48 (30%) | 12 (8%)
FPG (mg/dL)c
 | Baseline (mean) | 152 | 152 | 152
 | Change from baseline (adjusted mean) | -17 | -22 | 7
 | Difference from placebo + pioglitazone (adjusted mean) (97.5% CI) | -23b(-31.8, -15.2) | -28b(-36.7, -20.2) | --
Body Weight
 | Baseline mean in kg | 78 | 79 | 78
 | % change from baseline (adjusted mean) | -2.0 | -1.8 | 0.6
 | Difference from placebo (adjusted mean) (95% CI) | -2.6b(-3.4, -1.8) | -2.4b(-3.2, -1.6) | --
aModified intent to treat population. Last observation on study (LOCF) was used to impute missing data at Week 24. At Week 24, 10.9%, 8.3%, and 20.6% was imputed for patients randomized to JARDIANCE 10 mg, JARDIANCE 25 mg, and placebo, respectively.
bANCOVA p-value <0.0001 (HbA1c: ANCOVA model includes baseline HbA1c, treatment, renal function, and background medication. Body weight and FPG: same model used as for HbA1c but additionally including baseline body weight/baseline FPG, respectively.)
cFPG (mg/dL); for JARDIANCE 10 mg, n=163

Add-On Combination with Insulin with or without Metformin and/or Sulfonylureas
A total of 494 patients with type 2 diabetes inadequately controlled on insulin, or insulin in combination with oral drugs participated in a double-blind, placebo-controlled study to evaluate the efficacy of JARDIANCE as add-on therapy to insulin over 78 weeks.

Patients entered a 2-week placebo run-in period on basal insulin (e.g., insulin glargine, insulin detemir, or NPH insulin) with or without metformin and/or sulfonylurea background therapy. Following the run-in period, patients with inadequate glycemic control were randomized to the addition of JARDIANCE 10 mg, JARDIANCE 25 mg, or placebo. Patients were maintained on a stable dose of insulin prior to enrollment, during the run-in period, and during the first 18 weeks of treatment. For the remaining 60 weeks, insulin could be adjusted. The mean total daily insulin dose at baseline for JARDIANCE 10 mg, 25 mg, and placebo was 45 IU, 48 IU, and 48 IU, respectively.

JARDIANCE used in combination with insulin (with or without metformin and/or sulfonylurea) provided statistically significant reductions in HbA1c and FPG compared to placebo after both 18 and 78 weeks of treatment (see Table 10). JARDIANCE 10 mg or 25 mg daily also resulted in statistically significantly greater percent body weight reduction compared to placebo.

Table 10 Results at Week 18 and 78 for a Placebo-Controlled Study for JARDIANCE in Combination with Insulin
 |  | 18 weeks (no insulin adjustment) |  |  | 78 weeks (adjustable insulin dose after 18 weeks)
 |  | JARDIANCE 10 mg + Insulin N=169 | JARDIANCE 25 mg + Insulin N=155 | Placebo + Insulin N=170 | JARDIANCE 10 mg + Insulin N=169 | JARDIANCE 25 mg + Insulin N=155 | Placebo + Insulin N=170
HbA1c (%)a
 | Baseline (mean) | 8.3 | 8.3 | 8.2 | 8.3 | 8.3 | 8.2
 | Change from baseline (adjusted mean) | -0.6 | -0.7 | 0 | -0.4 | -0.6 | 0.1
 | Difference from placebo (adjusted mean) (97.5% CI) | -0.6b (-0.8, -0.4) | -0.7b (-0.9, -0.5) | -- | -0.5b (-0.7, -0.3) | -0.7b (-0.9, -0.5) | --
 | Patients (%) achieving HbA1c <7% | 18.0 | 19.5 | 5.5 | 12.0 | 17.5 | 6.7
FPG (mg/dL)
 | Baseline (mean) | 138 | 146 | 142 | 138 | 146 | 142
 | Change from baseline (adjusted mean, SE) | -17.9 (3.2) | -19.1 (3.3) | 10.4 (3.1) | -10.1 (3.2) | -15.2 (3.4) | 2.8 (3.2)
 | Difference from placebo (adjusted mean) (95% CI) | -28.2b(-37.0, -19.5) | -29.5b(-38.4, -20.6) | -- | -12.9c (-21.9, 3.9) | -17.9b (-27.0, -8.8) | --
Body Weight
 | Baseline mean in kg | 92 | 95 | 90 | 92 | 95 | 90
 | % change from baseline (adjusted mean) | -1.8 | -1.4 | -0.1 | -2.4 | -2.4 | 0.7
 | Difference from placebo (adjusted mean) (95% CI) | -1.7d (-3.0, -0.5) | -1.3e (-2.5, -0.0) | -- | -3.0b (-4.4, -1.7) | -3.0b (-4.4, -1.6) | --
aModified intent to treat population. Last observation on study (LOCF) was used to impute missing data at Week 18 and 78. At Week 18, 21.3%, 30.3%, and 21.8% was imputed for patients randomized to JARDIANCE 10 mg, JARDIANCE 25 mg, and placebo, respectively. At Week 78, 32.5%, 38.1% and 42.4% was imputed for patients randomized to JARDIANCE 10 mg, JARDIANCE 25 mg, and placebo, respectively.
bANCOVA p-value <0.0001 (HbA1c: ANCOVA model includes baseline HbA1c, treatment, and region; FPG: MMRM model includes baseline FPG, baseline HbA1c, treatment, region, visit and visit by treatment interaction. Body weight: MMRM model includes baseline body weight, baseline HbA1c, treatment, region, visit and visit by treatment interaction.
cp-value=0.0049
dp-value=0.0052
ep-value=0.0463

Add-on Combination with MDI Insulin with or without Metformin
A total of 563 patients with type 2 diabetes inadequately controlled on multiple daily injections (MDI) of insulin (total daily dose >60 IU), alone or in combination with metformin, participated in a double-blind, placebo-controlled study to evaluate the efficacy of JARDIANCE as add-on therapy to MDI insulin over 18 weeks.

Patients entered a 2-week placebo run-in period on MDI insulin with or without metformin background therapy. Following the run-in period, patients with inadequate glycemic control were randomized to the addition of JARDIANCE 10 mg, JARDIANCE 25 mg, or placebo. Patients were maintained on a stable dose of insulin prior to enrollment, during the run-in period, and during the first 18 weeks of treatment. The mean total daily insulin dose at baseline for JARDIANCE 10 mg, JARDIANCE 25 mg, and placebo was 88.6 IU, 90.4 IU, and 89.9 IU, respectively.

JARDIANCE 10 mg or 25 mg daily used in combination with MDI insulin (with or without metformin) provided statistically significant reductions in HbA1c compared to placebo after 18 weeks of treatment (see Table 11).

Table 11 Results at Week 18 for a Placebo-Controlled Study for JARDIANCE in Combination with Insulin and with or without Metformin
 | JARDIANCE 10 mg + Insulin +/- Metformin N=186 | JARDIANCE 25 mg + Insulin +/- Metformin N=189 | Placebo + Insulin +/- Metformin N=188
HbA1c (%)a
Baseline (mean) | 8.4 | 8.3 | 8.3
Change from baseline (adjusted mean) | -0.9 | -1.0 | -0.5
Difference from placebo (adjusted mean) (95% CI) | -0.4b(-0.6, -0.3) | -0.5b(-0.7, -0.4) | --
aModified intent to treat population. Last observation on study (LOCF) was used to impute missing data at Week 18. At Week 18, 23.7%, 22.8% and 23.4% was imputed for patients randomized to JARDIANCE 10 mg, JARDIANCE 25 mg, and placebo, respectively.
bANCOVA p-value <0.0001 (HbA1c: ANCOVA model includes baseline HbA1c, treatment, renal function, geographical region, and background medication).

During an extension period with treatment for up to 52 weeks, insulin could be adjusted to achieve defined glucose target levels. The change from baseline in HbA1c was maintained from 18 to 52 weeks with both JARDIANCE 10 mg and 25 mg. After 52 weeks, JARDIANCE 10 mg or 25 mg daily resulted in statistically greater percent body weight reduction compared to placebo (p-value <0.0001). The mean change in body weight from baseline was -1.95 kg for JARDIANCE 10 mg, and -2.04 kg for JARDIANCE 25 mg.

Renal Impairment
A total of 738 patients with type 2 diabetes and a baseline eGFR less than 90 mL/min/1.73 m^2participated in a randomized, double-blind, placebo-controlled, parallel-group to evaluate the efficacy and safety of JARDIANCE in patients with type 2 diabetes and renal impairment. The trial population comprised of 290 patients with mild renal impairment (eGFR 60 to less than 90 mL/min/1.73 m^2), 374 patients with moderate renal impairment (eGFR 30 to less than 60 mL/min/1.73 m^2), and 74 with severe renal impairment (eGFR less than 30 mL/min/1.73 m^2). A total of 194 patients with moderate renal impairment had a baseline eGFR of 30 to less than 45 mL/min/1.73 m^2and 180 patients a baseline eGFR of 45 to less than 60 mL/min/1.73 m^2.

At Week 24, JARDIANCE 25 mg provided statistically significant reduction in HbA1c relative to placebo in patients with mild to moderate renal impairment (see Table 12). A statistically significant reduction relative to placebo was also observed with JARDIANCE 25 mg in patients with either mild [-0.7 (95% CI: -0.9, -0.5)] or moderate [-0.4 (95% CI: -0.6, -0.3)] renal impairment and with JARDIANCE 10 mg in patients with mild [-0.5 (95% CI: -0.7, -0.3)] renal impairment.

The glucose lowering efficacy of JARDIANCE 25 mg decreased with decreasing level of renal function in the mild to moderate range. Least square mean Hb1Ac changes at 24 weeks were -0.6%, -0.5%, and -0.2% for those with a baseline eGFR of 60 to less than 90 mL/min/1.73 m^2, 45 to less than 60 mL/min/1.73 m^2, and 30 to less than 45 mL/min/1.73 m^2, respectively [see Dosage and Administration (2) and Use in Specific Populations (8.6)] . For placebo, least square mean HbA1c changes at 24 weeks were 0.1%, -0.1%, and 0.2% for patients with a baseline eGFR of 60 to less than 90 mL/min/1.73 m^2, 45 to less than 60 mL/min/1.73 m^2, and 30 to less than 45 mL/min/1.73 m^2, respectively.

Table 12 Results at Week 24 (LOCF) of Placebo-Controlled Study for JARDIANCE in Patients with Type 2 Diabetes and Renal Impairment
 |  | Mild and Moderate Impairmentb
 |  | JARDIANCE 25 mg
HbA1c
 | Number of patients | n=284
 | Comparison vs placebo (adjusted mean) (95% CI) | -0.5a(-0.6, -0.4)
ap-value <0.0001 (HbA1c: ANCOVA model includes baseline HbA1c, treatment, renal function, and background medication)
beGFR 30 to less than 90 mL/min/1.73 m^2- Modified intent to treat population. Last observation on study (LOCF) was used to impute missing data at Week 24. At Week 24, 24.6% and 26.2% was imputed for patients randomized to JARDIANCE 25 mg and placebo, respectively.

For patients with severe renal impairment, the analyses of changes in HbA1c and FPG showed no discernible treatment effect of JARDIANCE 25 mg compared to placebo [see Dosage and Administration (2.2) and Use in Specific Populations (8.6)] .

14.2 Cardiovascular Outcomes in Patients with Type 2 Diabetes Mellitus and Atherosclerotic Cardiovascular Disease

The effect of JARDIANCE on cardiovascular risk in adult patients with type 2 diabetes and established, stable, atherosclerotic cardiovascular disease was evaluated in the EMPA-REG OUTCOME study, a multicenter, multi-national, randomized, double-blind parallel group trial. The study compared the risk of experiencing a major adverse cardiovascular event (MACE) between JARDIANCE and placebo when these were added to and used concomitantly with standard of care treatments for diabetes and atherosclerotic cardiovascular disease. Coadministered antidiabetic medications were to be kept stable for the first 12 weeks of the trial. Thereafter, antidiabetic and atherosclerotic therapies could be adjusted, at the discretion of investigators, to ensure participants were treated according to the standard care for these diseases.

A total of 7020 patients were treated (JARDIANCE 10 mg = 2345; JARDIANCE 25 mg = 2342; placebo = 2333) and followed for a median of 3.1 years. Approximately 72% of the study population was Caucasian, 22% was Asian, and 5% was Black. The mean age was 63 years and approximately 72% were male.

All patients in the study had inadequately controlled type 2 diabetes mellitus at baseline (HbA1c greater than or equal to 7%). The mean HbA1c at baseline was 8.1% and 57% of participants had had diabetes for more than 10 years. Approximately 31%, 22% and 20% reported a past history of neuropathy, retinopathy and nephropathy to investigators respectively and the mean eGFR was 74 mL/min/1.73 m^2. At baseline, patients were treated with one (~30%) or more (~70%) antidiabetic medications including metformin (74%), insulin (48%), and sulfonylurea (43%).

All patients had established atherosclerotic cardiovascular disease at baseline including one (82%) or more (18%) of the following; a documented history of coronary artery disease (76%), stroke (23%) or peripheral artery disease (21%). At baseline, the mean systolic blood pressure was 136 mmHg, the mean diastolic blood pressure was 76 mmHg, the mean LDL was 86 mg/dL, the mean HDL was 44 mg/dL, and the mean urinary albumin to creatinine ratio (UACR) was 175 mg/g. At baseline, approximately 81% of patients were treated with renin angiotensin system inhibitors, 65% with beta-blockers, 43% with diuretics, 77% with statins, and 86% with antiplatelet agents (mostly aspirin).

The primary endpoint in EMPA-REG OUTCOME was the time to first occurrence of a Major Adverse Cardiac Event (MACE). A major adverse cardiac event was defined as occurrence of either a cardiovascular death or a nonfatal myocardial infarction (MI) or a nonfatal stroke. The statistical analysis plan had pre-specified that the 10 and 25 mg doses would be combined. A Cox proportional hazards model was used to test for non-inferiority against the pre-specified risk margin of 1.3 for the hazard ratio of MACE and superiority on MACE if non-inferiority was demonstrated. Type-1 error was controlled across multiples tests using a hierarchical testing strategy.

JARDIANCE significantly reduced the risk of first occurrence of primary composite endpoint of cardiovascular death, non-fatal myocardial infarction, or non-fatal stroke (HR: 0.86; 95% CI 0.74, 0.99). The treatment effect was due to a significant reduction in the risk of cardiovascular death in subjects randomized to empagliflozin (HR: 0.62; 95% CI 0.49, 0.77), with no change in the risk of non-fatal myocardial infarction or non-fatal stroke (see Table 13 and Figure 5 and 6). Results for the 10 mg and 25 mg empagliflozin doses were consistent with results for the combined dose groups.

Table 13 Treatment Effect for the Primary Composite Endpoint, and its Componentsa
 | Placebo N=2333 | JARDIANCE N=4687 | Hazard ratio vs placebo (95% CI)
Composite of cardiovascular death, non-fatal myocardial infarction, non-fatal stroke (time to first occurrence)b | 282 (12.1%) | 490 (10.5%) | 0.86 (0.74, 0.99)
Non-fatal myocardial infarctionc | 121 (5.2%) | 213 (4.5%) | 0.87 (0.70, 1.09)
Non-fatal strokec | 60 (2.6%) | 150 (3.2%) | 1.24 (0.92, 1.67)
Cardiovascular deathc | 137 (5.9%) | 172 (3.7%) | 0.62 (0.49, 0.77)
aTreated set (patients who had received at least one dose of study drug)
bp−value for superiority (2−sided) 0.04
cTotal number of events

The efficacy of JARDIANCE on cardiovascular death was generally consistent across major demographic and disease subgroups.

Vital status was obtained for 99.2% of subjects in the trial. A total of 463 deaths were recorded during the EMPA-REG OUTCOME trial. Most of these deaths were categorized as cardiovascular deaths. The non-cardiovascular deaths were only a small proportion of deaths, and were balanced between the treatment groups (2.1% in patients treated with JARDIANCE, and 2.4% of patients treated with placebo).

16 HOW SUPPLIED/STORAGE AND HANDLING

JARDIANCE tablets are available in 10 mg and 25 mg strengths as follows:

10 mg tablets:pale yellow, round, biconvex and bevel-edged, film-coated tablets debossed with “S 10” on one side and the Boehringer Ingelheim company symbol on the other side.
Bottles of 30 (NDC 0597-0152-30)
Bottles of 90 (NDC 0597-0152-90)
Cartons containing 3 blister cards of 10 tablets each (3 x 10) (NDC 0597-0152-37), institutional pack.

25 mg tablets:pale yellow, oval, biconvex film-coated tablets, debossed with “S 25” on one side and the Boehringer Ingelheim company symbol on the other side.
Bottles of 30 (NDC 0597-0153-30)
Bottles of 90 (NDC 0597-0153-90)
Cartons containing 3 blister cards of 10 tablets each (3 x 10) (NDC 0597-0153-37), institutional pack.

Dispense in a well-closed container as defined in the USP.

Storage
Store at 25°C (77°F); excursions permitted to 15°-30°C (59°-86°F)[see USP Controlled Room Temperature].

17 PATIENT COUNSELING INFORMATION

Advise the patient to read the FDA-approved patient labeling (Patient Information).

Instructions
Instruct patients to read the Patient Information before starting JARDIANCE therapy and to reread it each time the prescription is renewed. Instruct patients to inform their doctor or pharmacist if they develop any unusual symptom, or if any known symptom persists or worsens.

Inform patients of the potential risks and benefits of JARDIANCE and of alternative modes of therapy. Also inform patients about the importance of adherence to dietary instructions, regular physical activity, periodic blood glucose monitoring and HbA1c testing, recognition and management of hypoglycemia and hyperglycemia, and assessment for diabetes complications. Advise patients to seek medical advice promptly during periods of stress such as fever, trauma, infection, or surgery, as medication requirements may change.

Instruct patients to take JARDIANCE only as prescribed. If a dose is missed, it should be taken as soon as the patient remembers. Advise patients not to double their next dose.

Inform patients that the most common adverse reactions associated with the use of JARDIANCE are urinary tract infections and mycotic genital infections.

Advise pregnant women, and females of reproductive potential of the potential risk to a fetus with treatment with JARDIANCE [see Use in Specific Populations (8.1)] . Instruct females of reproductive potential to report pregnancies to their physicians as soon as possible.

Advise women that breastfeeding is not recommended during treatment with JARDIANCE [see Use in Specific Populations (8.2)].

Hypotension
Inform patients that hypotension may occur with JARDIANCE and advise them to contact their healthcare provider if they experience such symptoms [see Warnings and Precautions (5.1)] . Inform patients that dehydration may increase the risk for hypotension, and to have adequate fluid intake.

Ketoacidosis
Inform patients that ketoacidosis is a serious life-threatening condition. Cases of ketoacidosis have been reported during use of JARDIANCE. Instruct patients to check ketones (when possible) if symptoms consistent with ketoacidosis occur even if blood glucose is not elevated. If symptoms of ketoacidosis (including nausea, vomiting, abdominal pain, tiredness, and labored breathing) occur, instruct patients to discontinue JARDIANCE and seek medical advice immediately [see Warnings and Precautions (5.2)] .

Acute Kidney Injury
Inform patients that acute kidney injury has been reported during use of JARDIANCE. Advise patients to seek medical advice immediately if they have reduced oral intake (such as due to acute illness or fasting) or increased fluid losses (such as due to vomiting, diarrhea, or excessive heat exposure), as it may be appropriate to temporarily discontinue JARDIANCE use in those settings [see Warnings and Precautions (5.3)] .

Serious Urinary Tract Infections
Inform patients of the potential for urinary tract infections, which may be serious. Provide them with information on the symptoms of urinary tract infections. Advise them to seek medical advice if such symptoms occur [see Warnings and Precautions (5.4) ].

Genital Mycotic Infections in Females (e.g., Vulvovaginitis)
Inform female patients that vaginal yeast infections may occur and provide them with information on the signs and symptoms of vaginal yeast infections. Advise them of treatment options and when to seek medical advice [see Warnings and Precautions (5.6)] .

Genital Mycotic Infections in Males (e.g., Balanitis or Balanoposthitis)
Inform male patients that yeast infection of penis (e.g., balanitis or balanoposthitis) may occur, especially in uncircumcised males and patients with chronic and recurrent infections. Provide them with information on the signs and symptoms of balanitis and balanoposthitis (rash or redness of the glans or foreskin of the penis). Advise them of treatment options and when to seek medical advice [see Warnings and Precautions (5.6)] .

Hypersensitivity Reactions
Inform patients that serious hypersensitivity reactions, such as urticaria and angioedema, have been reported with JARDIANCE. Advise patients to report immediately any skin reaction or angioedema, and to discontinue drug until they have consulted prescribing physician [see Warnings and Precautions (5.7)] .

Laboratory Tests
Inform patients that renal function should be assessed prior to initiation of JARDIANCE and monitored periodically thereafter.

Inform patients that elevated glucose in urinalysis is expected when taking JARDIANCE.

Inform patients that response to all diabetic therapies should be monitored by periodic measurements of blood glucose and HbA1c levels, with a goal of decreasing these levels toward the normal range. Hemoglobin A1c monitoring is especially useful for evaluating long-term glycemic control.

Distributed by:
Boehringer Ingelheim Pharmaceuticals, Inc.
Ridgefield, CT 06877 USA

Marketed by:
Boehringer Ingelheim Pharmaceuticals, Inc.
Ridgefield, CT 06877 USA
and
Eli Lilly and Company
Indianapolis, IN 46285 USA

Licensed from:
Boehringer Ingelheim International GmbH, Ingelheim, Germany

Boehringer Ingelheim Pharmaceuticals, Inc. either owns or uses the Jardiance®and EMPA-REG OUTCOME®trademarks under license.

The other trademarks referenced are owned by third parties not affiliated with Boehringer Ingelheim Pharmaceuticals, Inc.

Copyright © 2017 Boehringer Ingelheim International GmbH
ALL RIGHTS RESERVED

IT5728RL112017

PATIENT INFORMATION
JARDIANCE®(jar DEE ans)
(empagliflozin)
Tablets

What is the most important information I should know about JARDIANCE?
JARDIANCE can cause serious side effects, including:

- Dehydration.JARDIANCE can cause some people to have dehydration (the loss of body water and salt). Dehydration may cause you to feel dizzy, faint, light-headed, or weak, especially when you stand up (orthostatic hypotension).
  You may be at higher risk of dehydration if you:
  - have low blood pressure
  - take medicines to lower your blood pressure, including diuretics (water pills)
  - are on low sodium (salt) diet
  - have kidney problems
  - are 65 years of age or older
- Vaginal yeast infection.Women who take JARDIANCE may get vaginal yeast infections. Symptoms of a vaginal yeast infection include:
  - vaginal odor
  - white or yellowish vaginal discharge (discharge may be lumpy or look like cottage cheese)
  - vaginal itching
- Yeast infection of the penis (balanitis or balanoposthitis).Men who take JARDIANCE may get a yeast infection of the skin around the penis. Certain men who are not circumcised may have swelling of the penis that makes it difficult to pull back the skin around the tip of the penis. Other symptoms of yeast infection of the penis include:
  - redness, itching, or swelling of the penis
  - rash of the penis
  - foul smelling discharge from the penis
  - pain in the skin around penis

Talk to your doctor about what to do if you get symptoms of a yeast infection of the vagina or penis. Your doctor may suggest you use an over-the-counter antifungal medicine. Talk to your doctor right away if you use an over-the-counter antifungal medication and your symptoms do not go away.

What is JARDIANCE?
- JARDIANCE is a prescription medicine used:
  - along with diet and exercise to lower blood sugar in adults with type 2 diabetes.
  - to reduce the risk of cardiovascular death in adults with type 2 diabetes who have known cardiovascular disease.
- JARDIANCE is not for people with type 1 diabetes.
- JARDIANCE is not for people with diabetic ketoacidosis (increased ketones in the blood or urine).
- It is not known if JARDIANCE is safe and effective in children under 18 years of age.

Who should not take JARDIANCE?

Do not take JARDIANCE if you:
- are allergic to empagliflozin or any of the ingredients in JARDIANCE. See the end of this leaflet for a list of ingredients in JARDIANCE.
- have severe kidney problems or are on dialysis

What should I tell my doctor before using JARDIANCE?

Before you take JARDIANCE, tell your doctor if you:
- have kidney problems
- have liver problems
- have a history of urinary tract infections or problems with urination
- are going to have surgery
- are eating less due to illness, surgery, or a change in your diet
- have or have had problems with your pancreas, including pancreatitis or surgery on your pancreas
- drink alcohol very often, or drink a lot of alcohol in the short term (“binge” drinking)
- have any other medical conditions
- are pregnant or plan to become pregnant. JARDIANCE may harm your unborn baby. If you become pregnant while taking JARDIANCE, tell your doctor as soon as possible. Talk with your doctor about the best way to control your blood sugar while you are pregnant.
- are breastfeeding or plan to breastfeed. JARDIANCE may pass into your breast milk and may harm your baby. Talk with your doctor about the best way to feed your baby if you are taking JARDIANCE. Do not breastfeed while taking JARDIANCE.

Tell your doctor about all the medicines you take,including prescription and over-the-counter medicines, vitamins, and herbal supplements.
JARDIANCE may affect the way other medicines work, and other medicines may affect how JARDIANCE works.

Especially tell your doctor if you take:
- diuretics (water pills)
- insulin or other medicines that can lower your blood sugar

Ask your doctor or pharmacist for a list of these medicines if you are not sure if your medicine is listed above.

How should I take JARDIANCE?

- Take JARDIANCE exactly as your doctor tells you to take it.
- Take JARDIANCE by mouth 1 time in the morning each day, with or without food.
- Your doctor may change your dose if needed.
- If you miss a dose, take it as soon as you remember. If you do not remember until it is time for your next dose, skip the missed dose and go back to your regular schedule. Do not take two doses of JARDIANCE at the same time. Talk with your doctor if you have questions about a missed dose.
- Your doctor may tell you to take JARDIANCE along with other diabetes medicines. Low blood sugar can happen more often when JARDIANCE is taken with certain other diabetes medicines. See “What are the possible side effects of JARDIANCE?”
- If you take too much JARDIANCE, call your doctor or go to the nearest hospital emergency room right away.
- When your body is under some types of stress, such as fever, trauma (such as a car accident), infection, or surgery, the amount of diabetes medicine that you need may change. Tell your doctor right away if you have any of these conditions and follow your doctor’s instructions.
- Check your blood sugar as your doctor tells you to.
- Stay on your prescribed diet and exercise program while taking JARDIANCE.
- Talk to your doctor about how to prevent, recognize and manage low blood sugar (hypoglycemia), high blood sugar (hyperglycemia), and complications of diabetes.
- Your doctor will check your diabetes with regular blood tests, including your blood sugar levels and your hemoglobin HbA1c.
- When taking JARDIANCE, you may have sugar in your urine, which will show up on a urine test.

What are the possible side effects of JARDIANCE?

JARDIANCE may cause serious side effects, including:
- See “ What is the most important information I should know about JARDIANCE?”
- Ketoacidosis (increased ketones in your blood or urine).Ketoacidosis has happened in people who have type 1 diabetes or type 2 diabetes,during treatment with JARDIANCE. Ketoacidosis is a serious condition, which may need to be treated in a hospital. Ketoacidosis may lead to death. Ketoacidosis can happen with JARDIANCE even if your blood sugar is less than 250 mg/dL. Stop taking JARDIANCE and call your doctor right away if you get any of the following symptoms:

- nausea
- vomiting
- stomach-area (abdominal) pain

- tiredness
- trouble breathing

If you get any of these symptoms during treatment with JARDIANCE, if possible, check for ketones in your urine, even if your
blood sugar is less than 250 mg/dL.

- Serious urinary tract infections.Serious urinary tract infections that may lead to hospitalization have happened in people who are taking JARDIANCE. Tell your doctor if you have any signs or symptoms of a urinary tract infection such as a burning feeling when passing urine, a need to urinate often, the need to urinate right away, pain in the lower part of your stomach (pelvis), or blood in the urine. Sometimes people also may have a fever, back pain, nausea or vomiting.
- Low blood sugar (hypoglycemia).If you take JARDIANCE with another medicine that can cause low blood sugar, such as a sulfonylurea or insulin, your risk of getting low blood sugar is higher. The dose of your sulfonylurea medicine or insulin may need to be lowered while you take JARDIANCE. Signs and symptoms of low blood sugar may include:

- headache
- drowsiness
- weakness

- irritability
- hunger
- fast heartbeat

- confusion
- shaking or feeling jittery

- dizziness
- sweating

- Kidney problems. Sudden kidney injury has happened to people taking JARDIANCE. Talk to your doctor right away if you:
  - reduce the amount of food or liquid you drink for example, if you are sick or cannot eat or
  - start to lose liquids from your body for example, from vomiting, diarrhea or being in the sun too long
- Allergic (hypersensitivity) reactions.Serious allergic reactions have happened in people who are taking JARDIANCE. Symptoms may include
  - swelling of your face, lips, throat and other areas of your skin
  - difficulty with swallowing or breathing.
  - raised, red areas on your skin (hives)
  If you have any of these symptoms, stop taking JARDIANCE and call your doctor right away or go to the nearest hospital emergency room.
- Increased fats in your blood (cholesterol)

These are not all the possible side effects of JARDIANCE. For more information, ask your doctor or pharmacist.
Call your doctor for medical advice about side effects. You may report side effects to FDA at 1-800-FDA-1088.

How should I store JARDIANCE?
Store JARDIANCE at room temperature 68°F to 77°F (20°C to 25°C).

General information about the safe and effective use of JARDIANCE.
Medicines are sometimes prescribed for purposes other than those listed in Patient Information. Do not use JARDIANCE for a condition for which it is not prescribed. Do not give JARDIANCE to other people, even if they have the same symptoms you have. It may harm them.
This Patient Information summarizes the most important information about JARDIANCE. If you would like more information, talk with your doctor. You can ask your pharmacist or doctor for information about JARDIANCE that is written for health professionals.
For more information about JARDIANCE, go to www.jardiance.com, scan the code below, or call Boehringer Ingelheim Pharmaceuticals, Inc. at 1-800-542-6257 or (TTY) 1-800-459-9906.

What are the ingredients in JARDIANCE?
Active Ingredient:empagliflozin
Inactive Ingredients:lactose monohydrate, microcrystalline cellulose, hydroxypropyl cellulose, croscarmellose sodium, colloidal silicon dioxide and magnesium stearate. In addition, the film coating contains the following inactive ingredients: hypromellose, titanium dioxide, talc, polyethylene glycol, and yellow ferric oxide.

Distributed by: Boehringer Ingelheim Pharmaceuticals, Inc.; Ridgefield, CT 06877 USA
Marketed by: Boehringer Ingelheim Pharmaceuticals, Inc.; Ridgefield, CT 06877 USA and Eli Lilly and Company, Indianapolis, IN 46285 USA
Licensed from: Boehringer Ingelheim International GmbH, Ingelheim, Germany
Boehringer Ingelheim Pharmaceuticals, Inc. either owns or uses the Jardiance®and EMPA-REG OUTCOME®trademarks under license.
The other trademarks referenced are owned by third parties not affiliated with Boehringer Ingelheim Pharmaceuticals, Inc.
Copyright © 2017 Boehringer Ingelheim International GmbH
ALL RIGHTS RESERVED
IT5728RL112017

This Patient Information has been approved by the U.S. Food and Drug Administration.

Revised: December 2017

REPACKAGING INFORMATION

Please reference the HOW SUPPLIED section listed above for a description of individual drug products listed below. This drug product has been received by Aphena Pharma Solutions - Tennessee, LLC in a manufacturer or distributor packaged configuration and repackaged in full compliance with all applicable cGMP regulations. The package configurations available from Aphena are listed below:

25mg
NDC 71610-177-15, Bottles of 15 Tablets
NDC 71610-177-45, Bottles of 45 Tablets
NDC 71610-177-81, Bottles of 1080 Tablets
NDC 71610-177-42, Bottles of 1800 Tablets
NDC 71610-177-99, Bottles of 5040 Tablets
NDC 71610-177-09, Bottles of 9000 Tablets

Store between 20°-25°C (68°-77°F). See USP Controlled Room Temperature. Dispense in a tight light-resistant container as defined by USP. Keep this and all drugs out of the reach of children.
Repackaged by:
Cookeville, TN 38506
20251027AMH

PRINCIPAL DISPLAY PANEL - 25 mg

NDC 71610-177 - Empagliflozin (Jardiance) 25 mg - Rx Only